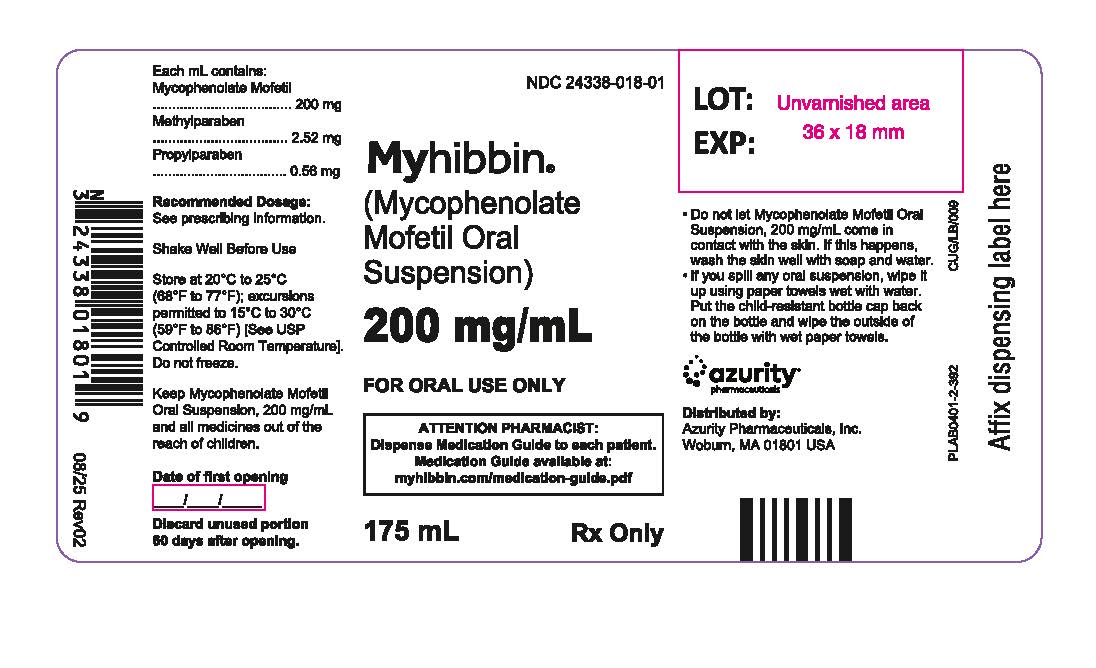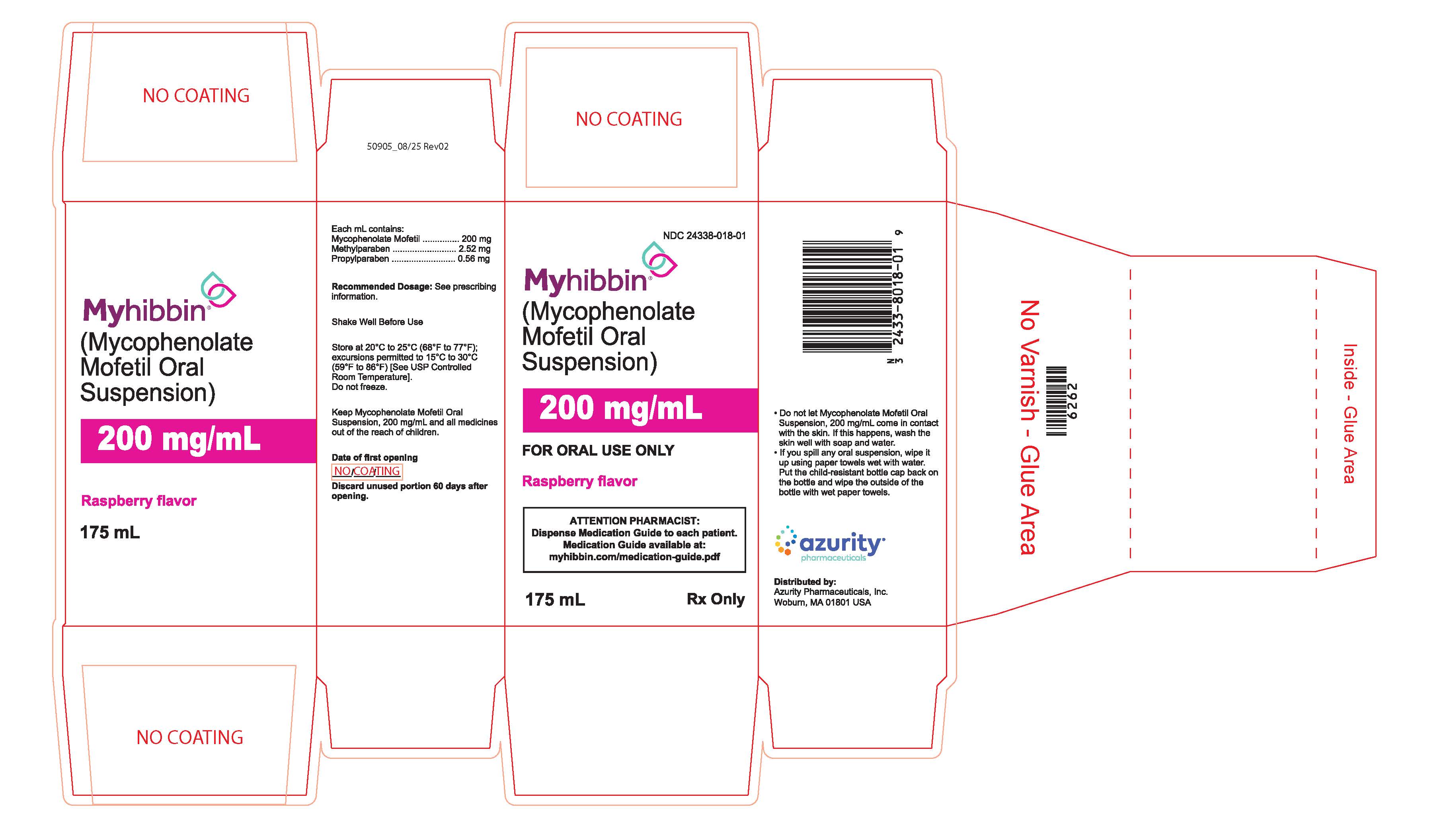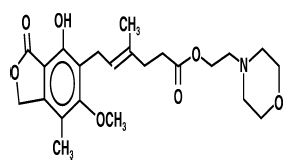 DRUG LABEL: MYHIBBIN
NDC: 24338-018 | Form: SUSPENSION
Manufacturer: Azurity Pharmaceuticals, Inc.
Category: prescription | Type: Human Prescription Drug Label
Date: 20250924

ACTIVE INGREDIENTS: MYCOPHENOLATE MOFETIL 200 mg/1 mL
INACTIVE INGREDIENTS: TRIETHYL CITRATE; DIMETHICONE; GLYCERIN; METHYLPARABEN; POLYSORBATE 80; PROPYLPARABEN; SORBITOL SOLUTION; SODIUM PHOSPHATE, MONOBASIC, UNSPECIFIED FORM; SODIUM PHOSPHATE, DIBASIC, UNSPECIFIED FORM; WATER; XANTHAN GUM

HIGHLIGHTS OF PRESCRIBING INFORMATION

These highlights do not include all the information needed to use MYHIBBIN safely and effectively. See full prescribing information for MYHIBBIN.
MYHIBBINTM (mycophenolate mofetil oral suspension)
Initial U.S. Approval: 1995

RECENT MAJOR CHANGES

Warnings and Precautions, Hypersensitivity Reactions (5.8) 4/2025

WARNING: EMBRYOFETAL TOXICITY, MALIGNANCIES and SERIOUS INFECTIONS

See full prescribing information for complete boxed warning

- Use during pregnancy is associated with increased risks of first trimester pregnancy loss and congenital malformations. Avoid if safer treatment options are available. Females of reproductive potential must be counseled regarding pregnancy prevention and planning [see Warnings and Precautions (5.1)].
- Increased risk of development of lymphoma and other malignancies, particularly of the skin [see Warnings and Precautions (5.2)] .
- Increased susceptibility to infections, including opportunistic infections and severe infections with fatal outcomes [see Warnings and Precautions (5.3)].

1 INDICATIONS AND USAGE

MYHIBBIN is an antimetabolite immunosuppressant indicated for the prophylaxis of organ rejection in adult and pediatric recipients 3 months of age and older of allogeneic kidney, heart or liver transplants, in combination with other immunosuppressants. (1)

2 DOSAGE AND ADMINISTRATION

ADULTS | DOSAGE
Kidney Transplant | 1 g orally twice daily (2.2)
Heart Transplant | 1.5 g orally twice daily (2.3)
Liver Transplant | 1.5 g orally twice daily (2.4)
PEDIATRICS
Kidney Transplant | 600 mg/m^2 orally twice daily, up to maximum of 2 g daily (2.2)
Heart Transplant | 600 mg/m^2 orally twice daily (starting dose) up to a maximum of 900 mg/m^2 twice daily (maximum daily dose of 3 g or 15 mL of oral suspension) (2.3)
Liver Transplant | 600 mg/m^2 orally twice daily (starting dose) up to a maximum of 900 mg/m^2 twice daily (maximum daily dose of 3 g or 15 mL of oral suspension) (2.4)

- Reduce or interrupt dosing in the event of neutropenia. (2.5)
- See full prescribing information (FPI) for: dosage modifications for renal impairment and neutropenia (2.5)

3 DOSAGE FORMS AND STRENGTHS

- Oral Suspension: 200 mg/mL mycophenolate mofetil.

4 CONTRAINDICATIONS

- History of hypersensitivity, including anaphylaxis, to mycophenolate mofetil, mycophenolic acid, polysorbate 80 or any component of the drug product (4)

5 WARNINGS AND PRECAUTIONS

- Blood Dyscrasias (Neutropenia, Red Blood Cell Aplasia): Monitor with blood tests; consider treatment interruption or dose reduction. (5.4)
- Gastrointestinal Complications: Monitor for complications such as bleeding, ulceration and perforations, particularly in patients with underlying gastrointestinal disorders. (5.5)
- Hypoxanthine-Guanine Phosphoribosyl-Transferase Deficiency: Avoid use of MYHIBBIN. (5.6)
- Acute Inflammatory Syndrome Associated with Mycophenolate Products: Monitor for this paradoxical inflammatory reaction. (5.7)
- Hypersensitivity Reactions: Discontinue MYHIBBIN; treat and monitor until signs and symptoms resolve. (5.8)
- Immunizations: Avoid live attenuated vaccines. (5.9)
- Blood Donation: Avoid during therapy and for 6 weeks thereafter. (5.10)
- Semen Donation: Avoid during therapy and for 90 days thereafter. (5.11)
- Potential Impairment on Driving and Use of Machinery: MYHIBBIN may affect ability to drive or operate machinery. (5.13)

6 ADVERSE REACTIONS

The most common adverse reactions in clinical trials (20 % or greater) include diarrhea, leukopenia, infection, vomiting, and there is evidence of a higher frequency of certain types of infections e.g., opportunistic infection. (6.1)

To report SUSPECTED ADVERSE REACTIONS, contact Azurity Pharmaceuticals, Inc. at 1-800-461-7449 or FDA at 1-800-FDA-1088 or www.fda.gov/medwatch.com.

7 DRUG INTERACTIONS

- See FPI for drugs that may interfere with systemic exposure and reduce MYHIBBIN efficacy: antacids with magnesium or aluminum hydroxide, proton pump inhibitors, drugs that interfere with enterohepatic recirculation, telmisartan, calcium-free phosphate binders. (7.1)
- MYHIBBIN may reduce effectiveness of oral contraceptives. Use of additional barrier contraceptive methods is recommended. (7.2)
- See FPI for other important drug interactions. (7)

8 USE IN SPECIFIC POPULATIONS

- Male Patients: Sexually active male patients and/or their female partners are recommended to use effective contraception during treatment of the male patient and for at least 90 days after cessation of treatment (8.3)

FULL PRESCRIBING INFORMATION

WARNING: EMBRYOFETAL TOXICITY, MALIGNANCIES and SERIOUS INFECTIONS

- Use during pregnancy is associated with increased risks of first trimester pregnancy loss and congenital malformations. Avoid if safer treatment options are available. Females of reproductive potential must be counseled regarding pregnancy prevention and planning [see Warnings and Precautions (5.1), Use in Special Populations (8.1, 8.3)] .
- Increased risk of development of lymphoma and other malignancies, particularly of the skin [see Warnings and Precautions (5.2)] .
- Increased susceptibility to bacterial, viral, fungal and protozoal infections, including opportunistic infections and viral reactivation of hepatitis B and C, which may lead to hospitalizations and fatal outcomes [see Warnings and Precautions (5.3)] .

1 INDICATIONS AND USAGE

MYHIBBIN is indicated for the prophylaxis of organ rejection, in adult and pediatric recipients 3 months of age and older of allogeneic kidney [see Clinical Studies (14.1)], heart [see Clinical Studies (14.2)] or liver transplants [see Clinical Studies (14.3)] , in combination with other immunosuppressants.

2 DOSAGE AND ADMINISTRATION

2.1 Important Administration Instructions

MYHIBBIN should not be used without the supervision of a physician with experience in immunosuppressive therapy.

MYHIBBIN should not be used interchangeably with mycophenolic acid delayed-release tablets without supervision of a physician with experience in immunosuppressive therapy because the rates of absorption following the administration of MYHIBBIN and mycophenolic acid delayed-release tablets are not equivalent.

Patients should avoid contact of the skin or mucous membranes with MYHIBBIN. If such contact occurs, they must wash the area of contact thoroughly with soap and water. In case of ocular contact, rinse eyes with plain water.

The initial oral dose of MYHIBBIN should be given as soon as possible following kidney, heart or liver transplant. It is recommended that MYHIBBIN be administered on an empty stomach. In stable transplant patients, however, MYHIBBIN may be administered with food if necessary [see Clinical Pharmacology (12.3)]. MYHIBBIN must not be mixed with any liquids prior to dose administration. If needed, MYHIBBIN can be administered via a nasogastric tube with a minimum size of 8 French (minimum 1.7 mm interior diameter).

Patients should be instructed to take a missed dose as soon as they remember, except if it is closer than 2 hours to the next scheduled dose; in this case, they should continue to take MYHIBBIN at the usual times.

2.2 Recommended Dosage for Kidney Transplant Patients

Adults

The recommended dosage for adult kidney transplant patients is 1 g orally, administered twice daily (total daily dose of 2 g).

Pediatrics Patients 3 months and older

Pediatric dosing is based on body surface area (BSA). The recommended dosage for pediatric kidney transplant patients 3 months and older is 600 mg/m ^2, administered twice daily (maximum daily dose of 2 g or 10 mL of the oral suspension).

2.3 Recommended Dosage for Heart Transplant Patients

Adults

The recommended dosage for adult heart transplant patients is 1.5 g orally administered twice daily (total daily dose of 3 g).

Pediatric Patients 3 months and older

The recommended starting dosage for pediatric heart transplant patients 3 months and older is 600 mg/m^2, administered twice daily. If well tolerated, the dose can be increased to a maintenance dosage of 900 mg/m^2 administered twice daily (maximum total daily dose of 3 g or 15 mL of the oral suspension). The dose may be individualized based on clinical assessment.

2.4 Recommended Dosage for Liver Transplant Patients

Adults

The recommended dosage for adult liver transplant patients is 1.5 g administered orally twice daily (total daily dose of 3 g).

Pediatrics Patients 3 months and older

The recommended starting dosage for pediatric liver transplant patients 3 months and older is 600 mg/m^2, administered twice daily. If well tolerated, the dose can be increased to a maintenance dosage of 900 mg/m^2 administered twice daily (maximum total daily dose of 3 g or 15 mL of the oral suspension). The dose may be individualized based on clinical assessment.

2.5 Dosage Modifications: Patients with Renal Impairment, Neutropenia

Renal Impairment

No dosage modifications are needed in kidney transplant patients with delayed graft function postoperatively [see Clinical Pharmacology (12.3)]. In kidney transplant patients with severe chronic impairment of the graft (GFR <25 mL/min/1.73 m ^2), do not administer doses of MYHIBBIN greater than 1 g twice a day. These patients should be carefully monitored [ see Clinical Pharmacology (12.3)].

Neutropenia

If neutropenia develops (ANC <1.3 x 10 ^3/µL), dosing with MYHIBBIN should be interrupted or reduced, appropriate diagnostic tests performed, and the patient managed appropriately [see Warnings and Precautions (5.4)and Adverse Reactions (6.1)].

3 DOSAGE FORMS AND STRENGTHS

Oral suspension: mycophenolate mofetil 200 mg/mL in a white to off-white suspension.

4 CONTRAINDICATIONS

MYHIBBIN is contraindicated in patients with a history of hypersensitivity, including anaphylaxis, to mycophenolate mofetil (MMF), mycophenolic acid (MPA), polysorbate 80 (TWEEN) or any other component of the drug product [see Warnings and Precautions (5.8)] .

5 WARNINGS AND PRECAUTIONS

5.1 Embryofetal Toxicity

Use of MMF during pregnancy is associated with an increased risk of first trimester pregnancy loss and an increased risk of congenital malformations, especially external ear and other facial abnormalities including cleft lip and palate, and anomalies of the distal limbs, heart, esophagus, kidney and nervous system. Females of reproductive potential must be made aware of these risks and must be counseled regarding pregnancy prevention and planning. Avoid use of MYHIBBIN during pregnancy if safer treatment options are available [see Use in Specific Populations (8.1, 8.3)].

5.2 Lymphoma and Other Malignancies

Patients receiving immunosuppressants, including MYHIBBIN, are at increased risk of developing lymphomas and other malignancies, particularly of the skin [see Adverse Reactions (6.1)]. The risk appears to be related to the intensity and duration of immunosuppression rather than to the use of any specific agent. For patients with increased risk for skin cancer, exposure to sunlight and UV light should be limited by wearing protective clothing and using a broad-spectrum sunscreen with a high protection factor.

Post-transplant lymphoproliferative disorder (PTLD) developed in 0.4% to 1% of patients receiving mycophenolate mofetil (2 g or 3 g) with other immunosuppressive agents in controlled clinical trials of kidney, heart and liver transplant patients [see Adverse Reactions (6.1)]. The majority of PTLD cases appear to be related to Epstein Barr Virus (EBV) infection. The risk of PTLD appears greatest in those individuals who are EBV seronegative, a population which includes many young children. In pediatric patients, no other malignancies besides PTLD were observed in clinical trials [see Adverse Reactions (6.1)].

5.3 Serious Infections

Patients receiving immunosuppressants, including MYHIBBIN, are at increased risk of developing bacterial, fungal, protozoal and new or reactivated viral infections, including opportunistic infections. The risk increases with the total immunosuppressive load. These infections may lead to serious outcomes, including hospitalizations and death [see Adverse Reactions (6.1, 6.2)].

Serious viral infections reported include:

- Polyomavirus-associated nephropathy (PVAN), especially due to BK virus infection
- JC virus-associated progressive multifocal leukoencephalopathy (PML), and
- Cytomegalovirus (CMV) infections: CMV seronegative transplant patients who receive an organ from a CMV seropositive donor are at highest risk of CMV viremia and CMV disease.
- Viral reactivation in patients infected with Hepatitis B and C
- COVID-19

Consider dose reduction or discontinuation of MYHIBBIN in patients who develop new infections or reactivate viral infections, weighing the risk that reduced immunosuppression represents to the functioning allograft.

PVAN, especially due to BK virus infection, is associated with serious outcomes, including deteriorating renal function and renal graft loss [see Adverse Reactions (6.2)]. Patient monitoring may help detect patients at risk for PVAN.

PML, which is sometimes fatal, commonly presents with hemiparesis, apathy, confusion, cognitive deficiencies, and ataxia [see Adverse Reactions (6.2)] . In immunosuppressed patients, physicians should consider PML in the differential diagnosis in patients reporting neurological symptoms.

The risk of CMV viremia and CMV disease is highest among transplant recipients seronegative for CMV at time of transplant who receive a graft from a CMV seropositive donor. Therapeutic approaches to limiting CMV disease exist and should be routinely provided. Patient monitoring may help detect patients at risk for CMV disease.

Viral reactivation has been reported in patients infected with HBV or HCV. Monitoring infected patients for clinical and laboratory signs of active HBV or HCV infection is recommended.

5.4 Blood Dyscrasias: Neutropenia and Pure Red Cell Aplasia (PRCA)

Severe neutropenia [absolute neutrophil count (ANC) <0.5 x 10 ^3/µL] developed in transplant patients receiving MMF 3 g daily [see Adverse Reactions (6.1)]. Patients receiving MYHIBBIN should be monitored for neutropenia .Neutropenia has been observed most frequently in the period from 31 to 180 days post-transplant in patients treated for prevention of kidney, heart and liver rejection. The development of neutropenia may be related to MYHIBBIN itself, concomitant medications, viral infections, or a combination of these causes. If neutropenia develops (ANC <1.3 x 10 ^3/µL), dosing with MYHIBBIN should be interrupted or the dose reduced, appropriate diagnostic tests performed, and the patient managed appropriately [see Dosage and Administration (2.5)].

Patients receiving MYHIBBIN should be instructed to report immediately any evidence of infection, unexpected bruising, bleeding or any other manifestation of bone marrow depression.

Consider monitoring with complete blood counts weekly for the first month, twice monthly for the second and third months, and monthly for the remainder of the first year.

Cases of pure red cell aplasia (PRCA) have been reported in patients treated with MMF in combination with other immunosuppressive agents. In some cases, PRCA was found to be reversible with dose reduction or cessation of MMF therapy. In transplant patients, however, reduced immunosuppression may place the graft at risk.

5.5 Gastrointestinal Complications

Gastrointestinal bleeding requiring hospitalization, ulceration and perforations were observed in clinical trials. Physicians should be aware of these serious adverse effects particularly when administering MYHIBBIN to patients with a gastrointestinal disease.

5.6 Patients with Hypoxanthine-Guanine Phosphoribosyl-Transferase Deficiency (HGPRT)

Mycophenolate mofetil is an inosine monophosphate dehydrogenase (IMPDH) inhibitor; therefore it should be avoided in patients with hereditary deficiencies of hypoxanthine-guanine phosphoribosyl-transferase (HGPRT) such as Lesch-Nyhan and Kelley-Seegmiller syndromes because it may cause an exacerbation of disease symptoms characterized by the overproduction and accumulation of uric acid leading to symptoms associated with gout such as acute arthritis, tophi, nephrolithiasis or urolithiasis and renal disease including renal failure.

5.7 Acute Inflammatory Syndrome Associated with Mycophenolate Products

Acute inflammatory syndrome (AIS) has been reported with the use of MMF and mycophenolate products, and some cases have resulted in hospitalization. AIS is a paradoxical pro-inflammatory reaction characterized by fever, arthralgias, arthritis, muscle pain and elevated inflammatory markers including, C-reactive protein and erythrocyte sedimentation rate, without evidence of infection or underlying disease recurrence. Symptoms occur within weeks to months of initiation of treatment or a dose increase. After discontinuation, improvement of symptoms and inflammatory markers are usually observed within 24 to 48 hours.

Monitor patients for symptoms and laboratory parameters of AIS when starting treatment with mycophenolate products or when increasing the dosage. Discontinue treatment and consider other treatment alternatives based on the risk and benefit for the patient.

5.8 Hypersensitivity Reactions

Postmarketing cases of hypersensitivity reactions, including angioedema and anaphylaxis, have been reported with the use of MMF and mycophenolate products. These reactions generally occurred within hours to the next day after initiating MMF or mycophenolate products. If signs or symptoms of a hypersensitivity reaction occur, discontinue MYHIBBIN; treat and monitor until signs and symptoms resolve [see Contraindications (4)].

5.9 Immunizations

During treatment with MYHIBBIN, the use of live attenuated vaccines should be avoided (e.g., intranasal influenza, measles, mumps, rubella, oral polio, BCG, yellow fever, varicella, and TY21a typhoid vaccines) and patients should be advised that vaccinations may be less effective. Advise patients to discuss with the physician before seeking any immunizations.

5.10 Blood Donation

Patients should not donate blood during therapy and for at least 6 weeks following discontinuation of MYHIBBIN because their blood or blood products might be administered to a female of reproductive potential or a pregnant woman.

5.11 Semen Donation

Based on animal data, men should not donate semen during therapy and for 90 days following discontinuation of MYHIBBIN [see Use In Specific Populations (8.3)] .

5.12 Effect of Concomitant Medications on Mycophenolic Acid Concentrations

A variety of drugs have potential to alter systemic MPA exposure when co-administered with MYHIBBIN. Therefore, determination of MPA concentrations in plasma before and after making any changes to immunosuppressive therapy, or when adding or discontinuing concomitant medications, may be appropriate to ensure MPA concentrations remain stable.

5.13 Potential Impairment of Ability to Drive or Operate Machinery

MYHIBBIN may impact the ability to drive and use machines. Patients should avoid driving or using machines if they experience somnolence, confusion, dizziness, tremor, or hypotension during treatment with MYHIBBIN [see Adverse Reactions (6.1)] .

6 ADVERSE REACTIONS

The following adverse reactions are discussed in greater detail in other sections of the label:
• Embryofetal Toxicity [see Warnings and Precautions (5.1)]
• Lymphomas and Other Malignancies [see Warnings and Precautions (5.2)]
• Serious Infections [see Warnings and Precautions (5.3)]
• Blood Dyscrasias: Neutropenia, Pure Red Cell Aplasia [see Warnings and Precautions (5.4)]
• Gastrointestinal Complications [see Warnings and Precautions (5.5)]
• Acute Inflammatory Syndrome Associated with Mycophenolate Products [see Warnings and Precautions (5.7)]
• Hypersensitivity Reactions [see Warnings and Precautions (5.8)]

6.1 Clinical Trials Experience

Because clinical trials are conducted under widely varying conditions, adverse reaction rates observed in the clinical trials of a drug cannot be directly compared to rates in the clinical trials of another drug and may not reflect the rates observed in practice.

An estimated total of 1557 adult patients received mycophenolate mofetil during pivotal clinical trials in the prevention of acute organ rejection. Of these, 991 were included in the three renal studies, 277 were included in one hepatic study, and 289 were included in one cardiac study. Patients in all study arms also received cyclosporine and corticosteroids.

The data described below primarily derive from five randomized, active-controlled double-blind 12-month trials of mycophenolate mofetil in de novo kidney (3) heart (1) and liver (1) transplant patients [see Clinical Studies (14.1, 14.2, and 14.3)] .

Oral Mycophenolate Mofetil

The incidence of adverse reactions for mycophenolate mofetil was determined in five randomized, comparative, double- blind trials in the prevention of rejection in kidney, heart and liver transplant patients (two active- and one placebo- controlled trials, one active-controlled trial, and one active-controlled trial, respectively) [see Clinical Studies (14.1, 14.2and 14.3)] .

The three de novo kidney studies with 12-month duration compared two dose levels of oral mycophenolate mofetil (1 g twice daily and 1.5 g twice daily) with azathioprine (2 studies) or placebo (1 study) when administered in combination with cyclosporine (Sandimmune®) and corticosteroids to prevent acute rejection episodes. One study also included anti-thymocyte globulin (ATGAM®) induction therapy.

In the de novo heart transplantation study with 12-month duration, patients received mycophenolate mofetil 1.5 g twice daily (n=289) or azathioprine 1.5 to 3 mg/kg/day (n=289), in combination with cyclosporine (Sandimmune® or Neoral®) and corticosteroids as maintenance immunosuppressive therapy.

In the de novo liver transplantation study with 12-month duration, patients received mycophenolate mofetil 1.5 g twice daily orally or azathioprine 1 to 2 mg/kg/day orally, in combination with cyclosporine (Neoral®) and corticosteroids as maintenance immunosuppressive therapy. The total number of patients enrolled was 565.

Approximately 53% of the kidney transplant patients, 65% of the heart transplant patients, and 48% of the liver transplant patients were treated for more than 1 year. Adverse reactions reported in ≥ 20% of patients in the mycophenolate mofetil treatment groups are presented below. The safety data of three kidney transplantation studies are pooled together.

Table 1 Adverse Reactions in Controlled Studies of De Novo Kidney, Heart or Liver Transplantation Reported in ≥20% of Patients in the Mycophenolate Mofetil (MMF) Group
System Organ Class | Kidney Studies |  |  | Heart Study |  | Liver Study
System Organ Class | MMF 2g/day (n=501) or 3g/day (n=490) | AZA 1 to 2 mg/kg/day or 100 to 150 mg/day | Placebo | MMF 3g/day | AZA 1.5 to 3 mg/kg/day | MMF 3g/day | AZA 1 to 2 mg/kg/day
Adverse Drug Reaction | (n=991) | (n=326) | (n=166) | (n=289) | (n=289) | (n=277) | (n=287)
 | % | % | % | % | % | % | %
Infections and infestations
Bacterial infections | 39.9 | 33.7 | 37.3 | - | - | 27.4 | 26.5
Viral infections | - a | - | - | 31.1 | 24.9 | - | -
Blood and lymphatic system disorders
Anemia | 20.0 | 23.6 | 2.4 | 45.0 | 47.1 | 43.0 | 53.0
Ecchymosis | - | - | - | 20.1 | 9.7 | - | -
Leukocytosis | - | - | - | 42.6 | 37.4 | 22.4 | 21.3
Leukopenia | 28.6 | 24.8 | 4.2 | 34.3 | 43.3 | 45.8 | 39.0
Thrombocytopenia | - | - | - | 24.2 | 28.0 | 38.3 | 42.2
Metabolism and nutrition disorders
Hypercholesterolemia | - | - | - | 46.0 | 43.9 | - | -
Hyperglycemia | - | - | - | 48.4 | 53.3 | 43.7 | 48.8
Hyperkalemia | - | - | - | - | - | 22.0 | 23.7
Hypocalcemia | - | - | - | - | - | 30.0 | 30.0
Hypokalemia | - | - | - | 32.5 | 26.3 | 37.2 | 41.1
Hypomagnesemia | - | - | - | 20.1 | 14.2 | 39.0 | 37.6
Psychiatric disorders
Depression | - | - | - | 20.1 | 15.2 | - | -
Insomnia | - | - | - | 43.3 | 39.8 | 52.3 | 47.0
Nervous system disorders
Dizziness | - | - | - | 34.3 | 33.9 | - | -
Headache | - | - | - | 58.5 | 55.4 | 53.8 | 49.1
Tremor | - | - | - | 26.3 | 25.6 | 33.9 | 35.5
Cardiac disorders
Tachycardia | - | - | - | 22.8 | 21.8 | 22.0 | 15.7
Vascular disorders
Hypertension | 27.5 | 32.2 | 19.3 | 78.9 | 74.0 | 62.1 | 59.6
Hypotension | - | - | - | 34.3 | 40.1 | - | -
Respiratory, thoracic and mediastinal disorders
Cough | - | - | - | 40.5 | 32.2 | - | -
Dyspnea | - | - | - | 44.3 | 44.3 | 31.0 | 30.3
Pleural effusion | - | - | - | - | - | 34.3 | 35.9
Gastrointestinal disorders
Abdominal pain | 22.4 | 23.0 | 11.4 | 41.9 | 39.4 | 62.5 | 51.2
Constipation | - | - | - | 43.6 | 38.8 | 37.9 | 38.3
Decreased appetite | - | - | - | - | - | 25.3 | 17.1
Diarrhea | 30.4 | 20.9 | 13.9 | 52.6 | 39.4 | 51.3 | 49.8
Dyspepsia | - | - | - | 22.1 | 22.1 | 22.4 | 20.9
Nausea | - | - | - | 56.1 | 60.2 | 54.5 | 51.2
Vomiting | - | - | - | 39.1 | 34.6 | 32.9 | 33.4
Hepatobiliary disorders
Blood lactate dehydrogenase increased | - | - | - | 23.5 | 18.3 | - | -
Hepatic enzyme increased | - | - | - | - | - | 24.9 | 19.2
Skin and subcutaneous tissues disorders
Rash | - | - | - | 26.0 | 20.8 | - | -
Renal and urinary disorders
Blood creatinine increased | - | - | - | 42.2 | 39.8 | - | -
Blood urea increased | - | - | - | 36.7 | 34.3 | - | -
General disorders and administration site conditions
Asthenia | - | - | - | 49.1 | 41.2 | 35.4 | 33.8
Edema b | 21.0 | 28.2 | 8.4 | 67.5 | 55.7 | 48.4 | 47.7
Pain c | 24.8 | 32.2 | 9.6 | 79.2 | 77.5 | 74.0 | 77.5
Pyrexia | - | - | - | 56.4 | 53.6 | 52.3 | 56.1

a:“-” Indicates that the incidence was below the cutoff value of 20% for inclusion in the table.
b:“Edema” includes peripheral edema, facial edema, scrotal edema.
c:“Pain” includes musculoskeletal pain (myalgia, neck pain, back pain).

In the three de novo kidney studies, patients receiving 2 g/day of mycophenolate mofetil had an overall better safety profile than did patients receiving 3 g/day of mycophenolate mofetil.

Post-transplant lymphoproliferative disease (PTLD, pseudolymphoma) developed in 0.4% to 1% of patients receiving mycophenolate mofetil (2 g or 3 g daily) with other immunosuppressive agents in controlled clinical trials of kidney, heart and liver transplant patients followed for at least 1 year [see Warnings and Precautions (5.2)]. Non- melanoma skin carcinomas occurred in 1.6% to 4.2% of patients, other types of malignancy in 0.7% to 2.1% of patients. Three-year safety data in kidney and heart transplant patients did not reveal any unexpected changes in incidence of malignancy compared to the 1-year data. In pediatric patients, PTLD was observed in 1.35% (2/148) by 12 months post-transplant.

Cytopenias, including leukopenia, anemia, thrombocytopenia and pancytopenia are a known risk associated with mycophenolate and may lead or contribute to the occurrence of infections and hemorrhages [see Warnings and Precautions (5.3)] . Severe neutropenia (ANC <0.5 x 10 ^3/µL) developed in up to 2% of kidney transplant patients, up to 2.8% of heart transplant patients and up to 3.6% of liver transplant patients receiving mycophenolate mofetil 3 g daily [see Warnings and Precautions (5.4)and Dosage and Administration (2.5)].

The most common opportunistic infections in patients receiving mycophenolate mofetil with other immunosuppressants were mucocutaneous candida, CMV viremia/syndrome, and herpes simplex. The proportion of patients with CMV viremia/syndrome was 13.5%. In patients receiving mycophenolate mofetil (2 g or 3 g) in controlled studies for prevention of kidney, heart or liver rejection, fatal infection/sepsis occurred in approximately 2% of kidney and heart patients and in 5% of liver patients [see Warnings and Precautions (5.3)]. The most serious gastrointestinal disorders reported were ulceration and hemorrhage, which are known risks associated with mycophenolate mofetil. Mouth, esophageal, gastric, duodenal, and intestinal ulcers often complicated by hemorrhage, as well as hematemesis, melena, and hemorrhagic forms of gastritis and colitis were commonly reported during the pivotal clinical trials, while the most common gastrointestinal disorders were diarrhea, nausea and vomiting. Endoscopic investigation of patients with mycophenolate mofetil-related diarrhea revealed isolated cases of intestinal villous atrophy [see Warnings and Precautions (5.5)] .

The following adverse reactions were reported with 3% to <20% incidence in kidney, heart, and liver transplant patients treated with mycophenolate mofetil, in combination with cyclosporine and corticosteroids.

Table 2 Adverse Reactions in Controlled Studies of De Novo Kidney, Heart or Liver Transplantation Reported in 3% to <20% of Patients Treated with Mycophenolate Mofetil in Combination with Cyclosporine and Corticosteroids
System Organ Class | Adverse Reactions
Body as a Whole | cellulitis, chills, hernia, malaise
Infections and Infestations | fungal infections
Hematologic and Lymphatic | coagulation disorder, ecchymosis, pancytopenia
Urogenital | hematuria
Cardiovascular | hypotension
Metabolic and Nutritional | acidosis, alkaline phosphatase increased, hyperlipemia, hypophosphatemia, weight loss
Digestive | esophagitis, flatulence, gastritis, gastrointestinal hemorrhage, hepatitis, ileus, nausea and vomiting, stomach ulcer, stomatitis
Neoplasm benign, malignant and unspecified | neoplasm
Skin and Appendages | skin benign neoplasm, skin carcinoma
Psychiatric | confusional state
Nervous | hypertonia, paresthesia, somnolence
Musculoskeletal | arthralgia, myasthenia

Pediatrics

The type and frequency of adverse events in a clinical study for prevention of kidney allograft rejection in 100 pediatric patients 3 months to 18 years of age dosed with mycophenolate mofetil oral suspension 600 mg/m ^2twice daily (up to 1 g twice daily) were generally similar to those observed in adult patients dosed with mycophenolate mofetil capsules at a dose of 1 g twice daily with the exception of abdominal pain, fever, infection, pain, sepsis, diarrhea, vomiting, pharyngitis, respiratory tract infection, hypertension, leukopenia, and anemia, which were observed in a higher proportion in pediatric patients.

Safety information in pediatric heart transplant or pediatric liver transplant patients treated with mycophenolate mofetil is supported by an open-label study in pediatric liver transplant patients and publications; the type and frequency of the reported adverse reactions are consistent with those observed in pediatric patients following renal transplant and in adults.

Geriatrics

Geriatric patients (≥65 years), particularly those who are receiving mycophenolate mofetil as part of a combination immunosuppressive regimen, may be at increased risk of certain infections (including cytomegalovirus [CMV] tissue invasive disease) and possibly gastrointestinal hemorrhage and pulmonary edema, compared to younger individuals [see Warnings and Precautions (5.3)and Adverse Reactions (6.1)].

6.2 Postmarketing Experience

The following adverse reactions have been identified during post-approval use of mycophenolate mofetil. Because these reactions are reported voluntarily from a population of uncertain size, it is not always possible to reliably estimate their frequency or establish a causal relationship to drug exposure:

- Embryo-Fetal Toxicity: Congenital malformations and spontaneous abortions, mainly in the first trimester, have been reported following exposure to mycophenolate mofetil (MMF) in combination with other immunosuppressants during pregnancy [see Warnings and Precautions (5.1), and Use in Specific Populations (8.1), (8.3)]. Congenital malformations include:

- Facial malformations: cleft lip, cleft palate, micrognathia, hypertelorism of the orbits

- Abnormalities of the ear and eye: abnormally formed or absent external/middle ear, coloboma, microphthalmos

- Malformations of the fingers: polydactyly, syndactyly, brachydactyly

- Cardiac abnormalities: atrial and ventricular septal defects

- Esophageal malformations: esophageal atresia

- Nervous system malformations: such as spina bifida.

- Digestive: Colitis, pancreatitis
- Hematologic and Lymphatic: Bone marrow failure, cases of pure red cell aplasia (PRCA) and hypogammaglobulinemia have been reported in patients treated with mycophenolate mofetil in combination with other immunosuppressive agents [see Warnings and Precautions (5.4)].
- Immune: Hypersensitivity reactions, including anaphylaxis and angioedema [see Warnings and Precautions (5.8)] , hypogammaglobinemia.
- Infections: Meningitis, infectious endocarditis, tuberculosis, atypical mycobacterial infection, progressive multifocal leukoencephalopathy, BK virus infection, viral reactivation of hepatitis B and hepatitis C, protozoal infections [see Warnings and Precautions (5.3)].
- Respiratory: Bronchiectasis, interstitial lung disease, fatal pulmonary fibrosis, have been reported rarely and should be considered in the differential diagnosis of pulmonary symptoms ranging from dyspnea to respiratory failure in post-transplant patients receiving mycophenolate mofetil.
- Vascular: Lymphocele

7 DRUG INTERACTIONS

7.1 Effect of Other Drugs on MYHIBBIN

Table 3 Drug Interactions with MYHIBBIN that Affect Mycophenolic Acid (MPA) Exposure
Antacids with Magnesium or Aluminum Hydroxide
Clinical Impact | Concomitant use with an antacid containing magnesium or aluminum hydroxide decreases MPA systemic exposure [see Clinical Pharmacology (12.3)] , which may reduce MYHIBBIN efficacy.
Prevention or Management | Administer magnesium or aluminum hydroxide containing antacids at least 2h after MYHIBBIN.
Proton Pump Inhibitors (PPIs)
Clinical Impact | Concomitant use with PPIs decreases MPA systemic exposure [see Clinical Pharmacology (12.3)] , which may reduce MYHIBBIN efficacy.
Prevention or Management | Monitor patients for alterations in efficacy when PPIs are co- administered with MYHIBBIN.
Examples | Lansoprazole, pantoprazole
Drugs that Interfere with Enterohepatic Recirculation
Clinical Impact | Concomitant use with drugs that directly interfere with enterohepatic recirculation, or indirectly interfere with enterohepatic recirculation by altering the gastrointestinal flora, can decrease MPA systemic exposure [see Clinical Pharmacology (12.3)] , which may reduce MYHIBBIN efficacy.
Prevention or Management | Monitor patients for alterations in efficacy or MYHIBBIN-related adverse reactions when these drugs are co-administered with MYHIBBIN.
Examples | Cyclosporine A, trimethoprim/sulfamethoxazole, bile acid sequestrants (cholestyramine), rifampin as well as aminoglycoside, cephalosporin, fluoroquinolone and penicillin classes of antimicrobials
Drugs Modulating Glucuronidation
Clinical Impact | Concomitant use with drugs inducing glucuronidation decreases MPA systemic exposure, potentially reducing MYHIBBIN efficacy, while use with drugs inhibiting glucuronidation increases MPA systemic exposure [see Clinical Pharmacology (12.3)] , which may increase the risk of MYHIBBIN-related adverse reactions.
Prevention or Management | Monitor patients for alterations in efficacy or MYHIBBIN-related adverse reactions when these drugs are co-administered with MYHIBBIN.
Examples | Telmisartan (induces glucuronidation); isavuconazole (inhibits glucuronidation).
Calcium Free Phosphate Binders
Clinical Impact | Concomitant use with calcium free phosphate binders decrease MPA systemic exposure [see Clinical Pharmacology (12.3)] , which may reduce MYHIBBIN efficacy.
Prevention or Management | Administer calcium free phosphate binders at least 2 hours after MYHIBBIN.
Examples | Sevelamer

7.2 Effect of MYHIBBIN on Other Drugs

Table 4 Drug Interactions with MYHIBBIN that Affect Other Drugs
Drugs that Undergo Renal Tubular Secretion
Clinical Impact | When concomitantly used with MYHIBBIN, its metabolite MPAG, may compete with drugs eliminated by renal tubular secretion which may increase plasma concentrations and/or adverse reactions associated with these drugs.
Prevention or Management | Monitor for drug-related adverse reactions in patients with renal impairment.
Examples | Acyclovir, ganciclovir, probenecid, valacyclovir, valganciclovir
Combination Oral Contraceptives
Clinical Impact | Concomitant use with mycophenolate mofetil decreased the systemic exposure to levonorgestrel, but did not affect the systemic exposure to ethinylestradiol [see Clinical Pharmacology (12.3)] , which may result in reduced combination oral contraceptive effectiveness.
Prevention or Management | Use additional barrier contraceptive methods.

8 USE IN SPECIFIC POPULATIONS

8.1 Pregnancy

Pregnancy Exposure Registry

There is a pregnancy exposure registry that monitors pregnancy outcomes in women exposed to mycophenolate during pregnancy and those becoming pregnant within 6 weeks of discontinuing MYHIBBIN treatment. To report a pregnancy or obtain information about the registry, visit the Mycophenolate Pregnancy Registry at www.mycophenolateREMS.com or call 1-800-617-8191.

Risk Summary

Use of mycophenolate mofetil (MMF) during pregnancy is associated with an increased risk of first trimester pregnancy loss and an increased risk of multiple congenital malformations in multiple organ systems (see Human Data). Oral administration of mycophenolate to rats and rabbits during the period of organogenesis produced congenital malformations and pregnancy loss at doses less than the recommended clinical dose (0.01 to 0.05 times the recommended clinical doses in kidney and heart transplant patients) (see Animal Data). Consider alternative immunosuppressants with less potential for embryofetal toxicity. Risks and benefits of MYHIBBIN should be discussed with the pregnant woman. The background risk of pregnancy loss and congenital malformations in organ transplant populations is not clear. In the U.S. general population, the estimated background risk of major birth defects and miscarriage in clinically recognized pregnancies is 2 to 4% and 15 to 20%, respectively.

Data

Human Data

A spectrum of congenital malformations (including multiple malformations in individual newborns) has been reported in 23 to 27% of live births in MMF exposed pregnancies, based on published data from pregnancy registries. Malformations that have been documented include external ear, eye, and other facial abnormalities including cleft lip and palate, and anomalies of the distal limbs, heart, esophagus, kidney, and nervous system.

Based on published data from pregnancy registries, the risk of first trimester pregnancy loss has been reported at 45 to 49% following MMF exposure.

Animal Data

In animal reproductive toxicology studies, there were increased rates of fetal resorptions and malformations in the absence of maternal toxicity. Oral administration of MMF to pregnant rats from Gestational Day 7 to Day 16 produced increased embryofetal lethality and fetal malformations including anophthalmia, agnathia, and hydrocephaly at doses equivalent to 0.015 and 0.01 times the recommended human doses for renal and cardiac transplant patients, respectively, when corrected for BSA. Oral administration of MMF to pregnant rabbits from Gestational Day 7 to Day 19 produced increased embryofetal lethality and fetal malformations included ectopia cordis, ectopic kidneys, diaphragmatic hernia, and umbilical hernia at dose equivalents as low as 0.05 and 0.03 times the recommended human doses for renal and cardiac transplant patients, respectively, when corrected for BSA.

8.2 Lactation

Risk Summary

There are no data on the presence of mycophenolate in human milk, or the effects on milk production. There are limited data in the National Transplantation Pregnancy Registry on the effects of mycophenolate on a breastfed child (see Data). Studies in rats treated with MMF have shown mycophenolic acid (MPA) to be present in milk. Because available data are limited, it is not possible to exclude potential risks to a breastfeeding infant. The developmental and health benefits of breastfeeding should be considered along with the mother’s clinical need for MYHIBBIN and any potential adverse effects on the breastfed infant from MYHIBBIN or from the underlying maternal condition.

Data

Limited information is available from the National Transplantation Pregnancy Registry. Of seven infants reported by the National Transplantation Pregnancy Registry to have been breastfed while the mother was taking mycophenolate, all were born at 34-40 weeks gestation, and breastfed for up to 14 months. No adverse events were reported.

8.3 Females and Males of Reproductive Potential

Females of reproductive potential must be made aware of the increased risk of first trimester pregnancy loss and congenital malformations and must be counseled regarding pregnancy prevention and planning.

Pregnancy Planning

For patients who are considering pregnancy, consider alternative immunosuppressants with less potential for embryofetal toxicity whenever possible. Risks and benefits of MYHIBBIN should be discussed with the patient.

Pregnancy Testing

To prevent unplanned exposure during pregnancy, all females of reproductive potential should have a serum or urine pregnancy test with a sensitivity of at least 25 mlU/mL immediately before starting MYHIBBIN. Another pregnancy test with the same sensitivity should be done 8 to 10 days later. Repeat pregnancy tests should be performed during routine follow-up visits. Results of all pregnancy tests should be discussed with the patient. In the event of a positive pregnancy test, consider alternative immunosuppressants with less potential for embryofetal toxicity whenever possible.

Contraception

Female Patients

Females of reproductive potential taking MYHIBBIN must receive contraceptive counseling and use acceptable contraception (see Table 5 for acceptable contraception methods). Patients must use acceptable birth control during the entire MYHIBBIN therapy, and for 6 weeks after stopping MYHIBBIN, unless the patient chooses abstinence.

Patients should be aware that MYHIBBIN reduces blood levels of the hormones from the oral contraceptive pill and could theoretically reduce its effectiveness [see Drug Interactions (7.2)].

Table 5 Acceptable Contraception Methods for Females of Reproductive Potential Pick from the following birth control options:
Option 1
Methods to Use Alone | - Intrauterine devices (IUDs) - Tubal sterilization - Patient’s partner vasectomy
OR
Option 2 | Hormone Methods choose 1 |  | Barrier Methods choose 1
Choose One Hormone Method AND One Barrier Method | Estrogen and Progesterone; - Oral Contraceptive Pill - Transdermal patch - Vaginal ring; Progesterone-only; - Injection - Implant | AND | - Diaphragm with spermicide - Cervical cap with spermicide - Contraceptive sponge - Male condom - Female condom
OR
Option 3 | Barrier Methods choose 1 |  | Barrier Methods choose 1
Choose One Barrier Method from each column (must choose two methods) | - Diaphragm with spermicide - Cervical cap with spermicide - Contraceptive sponge | AND | - Male condom - Female condom

Male Patients Genotoxic effects have been observed in animal studies at exposures exceeding the human therapeutic exposures by approximately 1.25 times. Thus, the risk of genotoxic effects on sperm cells cannot be excluded. Based on this potential risk, sexually active male patients and/or their female partners are recommended to use effective contraception during treatment of the male patient and for at least 90 days after cessation of treatment. Also, based on the potential risk of genotoxic effects, male patients should not donate sperm during treatment with MYHIBBIN and for at least 90 days after cessation of treatment [ see Use in Special Populations (8.1), Nonclinical Toxicology (13.1), Patient Counseling Information (17.9)].

8.4 Pediatric Use

Safety and effectiveness have been established in pediatric patients 3 months and older for the prophylaxis of organ rejection of allogenic kidney, heart or liver transplants.

Kidney Transplant

Use of MYHIBBIN in this population is supported by evidence from adequate and well-controlled studies of mycophenolate mofetil in adults with additional data from one open-label, pharmacokinetic and safety study of mycophenolate mofetil in pediatric patients after receiving allogeneic kidney transplant (100 patients, 3 months to 18 years of age) [see Dosage and Administration (2.2), Adverse Reactions (6.1), Clinical Pharmacology (12.3), Clinical Studies (14.1)].

Heart Transplant and Liver Transplant

Use of MYHIBBIN in pediatric heart transplant and liver transplant patients is supported by adequate and well-controlled studies and pharmacokinetic data in adult heart transplant and liver transplant patients. Additional supportive data include pharmacokinetic data in pediatric kidney transplant and pediatric liver transplant patients (8 liver transplant patients, 9 months to 5 years of age, in an open-label, pharmacokinetic and safety study) and published evidence of clinical efficacy and safety in pediatric heart transplant and pediatric liver transplant patients [see Dosage and Administration (2.3, 2.4), Adverse Reactions (6.1), Clinical Pharmacology (12.3), Clinical Studies (14.1)].

The combination of inactive ingredients (e.g., simethicone, sodium phosphate monobasic dihydrate, sodium phosphate dibasic dihydrate, glycerin) in MYHIBBIN have the potential to impact gastrointestinal tolerability. Monitor pediatric patients receiving MYHIBBIN for signs and symptoms of gastrointestinal intolerance.

8.5 Geriatric Use

Clinical studies of mycophenolate mofetil did not include sufficient numbers of subjects aged 65 and over to determine whether they respond differently from younger subjects. Other reported clinical experience has not identified differences in responses between geriatric and younger patients. In general, dose selection for a geriatric patient should take into consideration the presence of decreased hepatic, renal or cardiac function and of concomitant drug therapies. [see Adverse Reactions (6.1), Drug Interactions (7)].

8.6 Patients with Renal Impairment

Patients with Kidney Transplant

No dosage adjustments are needed in kidney transplant patients experiencing delayed graft function postoperatively, but patients should be carefully monitored [see Clinical Pharmacology (12.3)]. In kidney transplant patients with severe chronic impairment of the graft (GFR <25 mL/min/1.73 m^2), no dose adjustments are necessary; however, doses greater than 1 g administered twice a day should be avoided.

Patients with Heart and Liver Transplant

No data are available for heart or liver transplant patients with severe chronic renal impairment. MYHIBBIN may be used for heart or liver transplant patients with severe chronic renal impairment if the potential benefits outweigh the potential risks.

8.7 Patients with Hepatic Impairment

Patients with Kidney Transplant
No dosage adjustments are recommended for kidney transplant patients with severe hepatic parenchymal disease. However, it is not known whether dosage adjustments are needed for hepatic disease with other etiologies [see Clinical Pharmacology (12.3)].
Patients with Heart Transplant
No data are available for heart transplant patients with severe hepatic parenchymal disease.

10 OVERDOSAGE

Possible signs and symptoms of acute overdose include hematological abnormalities such as leukopenia and neutropenia, and gastrointestinal symptoms such as abdominal pain, diarrhea, nausea, vomiting, and dyspepsia.

The experience with overdose of mycophenolate mofetil in humans is limited. The reported effects associated with overdose fall within the known safety profile of the drug. The highest dose administered to kidney transplant patients in clinical trials has been 4 g/day. In limited experience with heart and liver transplant patients in clinical trials, the highest doses used were 4 g/day or 5 g/day. At doses of 4 g/day or 5 g/day, there appears to be a higher rate, compared to the use of 3 g/day or less, of gastrointestinal intolerance (nausea, vomiting, and/or diarrhea), and occasional hematologic abnormalities, particularly neutropenia [see Warnings and Precautions (5.4)] .

Treatment and Management

MPA and the phenolic glucuronide metabolite of MPA (MPAG) are usually not removed by hemodialysis. However, at high MPAG plasma concentrations (>100 µg/mL), small amounts of MPAG are removed. By increasing excretion of the drug, MPA can be removed by bile acid sequestrants, such as cholestyramine [see Clinical Pharmacology (12.3)].

11 DESCRIPTION

MYHIBBIN (mycophenolate mofetil) is an antimetabolite immunosuppressant. It is the 2-morpholinoethyl ester of mycophenolic acid (MPA), an immunosuppressive agent; inosine monophosphate dehydrogenase (IMPDH) inhibitor.

The chemical name for mycophenolate mofetil (MMF) is 4-Hexenoic acid, 6-(1,3-dihydro-4-hydroxy-6-methoxy-7-methyl-3-oxo-5-isobenzofuranyl)-4-methyl-,2-(4-morpholinyl) ethyl ester, (E)-. It has an empirical formula of C23H31NO7, a molecular weight of 433.49, and the following structural formula:

MMF is a white or almost white, crystalline powder. It is slightly soluble in water (43 µg/mL at pH 7.4); the solubility increases in acidic medium (4.27 mg/mL at pH 3.6).

The drug product is an oral suspension that contains 200 mg of mycophenolate mofetil/mL. The pH of suspension is between 6 and 8.

Inactive ingredients in MYHIBBIN include dibasic sodium phosphate, glycerin, methylparaben, monobasic sodium phosphate, polysorbate 80, propylparaben, purified water, raspberry flavor, simethicone emulsion, sorbitol solution, and xanthan gum.

12 CLINICAL PHARMACOLOGY

12.1 Mechanism of Action

Mycophenolate mofetil (MMF) is absorbed following oral administration and hydrolyzed to mycophenolic acid (MPA), the active metabolite. MPA is a selective uncompetitive inhibitor of the two isoforms (type I and type II) of inosine monophosphate dehydrogenase (IMPDH) leading to inhibition of the de novo pathway of guanosine nucleotide synthesis and blocks DNA synthesis. The mechanism of action of MPA is multifaceted and includes effects on cellular checkpoints responsible for metabolic programming of lymphocytes. MPA shifts transcriptional activities in lymphocytes from a proliferative state to catabolic processes. In vitro studies suggest that MPA modulates transcriptional activities in human CD4+ T-lymphocytes by suppressing the Akt/mTOR and STAT5 pathways that are relevant to metabolism and survival, leading to an anergic state of T-cells whereby the cells become less responsive to antigenic stimulation. Additionally, MPA enhanced the expression of negative co-stimulators such as CD70, PD-1, CTLA-4, and transcription factor FoxP3 as well as decreased the expression of positive co-stimulators CD27 and CD28.

MPA decreases proliferative responses of T- and B-lymphocytes to both mitogenic and allo-antigenic stimulation, antibody responses, as well as the production of cytokines from lymphocytes and monocytes such as GM-CSF, IFN-Ɣ, IL-17, and TNF-α. Additionally, MPA prevents the glycosylation of lymphocyte and monocyte glycoproteins that are involved in intercellular adhesion to endothelial cells and may inhibit recruitment of leukocytes into sites of inflammation and graft rejection.

Overall, the effect of MPA is cytostatic and reversible.

12.2 Pharmacodynamics

There is a lack of information regarding the pharmacodynamic effects of MMF.

12.3 Pharmacokinetics

Absorption

Following oral administration, MMF undergoes complete conversion to MPA, the active metabolite. In 12 healthy volunteers, the mean absolute bioavailability of oral MMF relative to intravenous MMF was 94%.

The mean (±SD) pharmacokinetic parameters estimates for MPA following the administration of MMF given as single doses to healthy volunteers, and multiple doses to kidney, heart, and liver transplant patients, are shown in Table 6. The area under the plasma-concentration time curve (AUC) for MPA appears to increase in a dose-proportional fashion in kidney transplant patients receiving multiple oral doses of MMF up to a daily dose of 3 g (1.5g twice daily) (see Table 6).

Table 6 Pharmacokinetic Parameters for MPA [mean (±SD)] Following Administration of MMF to Healthy Volunteers (Single Dose), and Kidney, Heart, and Liver Transplant Patients (Multiple Doses)
Healthy Volunteers | Dose/Route | T max (h) | C max (mcg/mL) | Total AUC (mcg∙h/mL)
Single dose | 1 g/oral | 0.80 (±0.36) (n=129) | 24.5 (±9.5) (n=129) | 63.9 (±16.2) (n=117)
Kidney Transplant Patients (twice daily dosing) Time After Transplantation | Dose/Route | T max (h) | C max (mcg/mL) | Interdosing Interval AUC(0-12h) (mcg∙h/mL)
5 days | 1 g | 1.58 (±0.46) (n=31) | 12.0 (±3.82) (n=31) | 40.8 (±11.4) (n=31)
6 days | 1 g/oral | 1.33 (±1.05) (n=31) | 10.7 (±4.83) (n=31) | 32.9 (±15.0) (n=31)
Early (Less than 40 days) | 1 g/oral | 1.31 (±0.76) (n=25) | 8.16 (±4.50) (n=25) | 27.3 (±10.9) (n=25)
Early (Less than 40 days) | 1.5 g/oral | 1.21 (±0.81) (n=27) | 13.5 (±8.18) (n=27) | 38.4 (±15.4) (n=27)
Late (Greater than 3 months) | 1.5 g/oral | 0.90 (±0.24) (n=23) | 24.1 (±12.1) (n=23) | 65.3 (±35.4) (n=23)
Heart Transplant Patients (twice daily dosing) Time After Transplantation | Dose/Route | T max (h) | C max (mcg/mL) | Interdosing Interval AUC(0-12h) (mcg∙h/mL)
Early (Day before discharge) | 1.5 g/oral | 1.8 (±1.3) (n=11) | 11.5 (±6.8) (n=11) | 43.3 (±20.8) (n=9)
Late (Greater than 6 months) | 1.5 g/oral | 1.1 (±0.7) (n=52) | 20.0 (±9.4) (n=52) | 54.1 a (±20.4) (n=49)
Liver Transplant Patients (twice daily dosing) Time After Transplantation | Dose/Route | T max (h) | C max (mcg/mL) | Interdosing Interval AUC(0-12h) (mcg∙h/mL)
4 to 9 days | 1 g | 1.50 (±0.517) (n=22) | 17.0 (±12.7) (n=22) | 34.0 (±17.4) (n=22)
Early (5 to 8 days) | 1.5 g/oral | 1.15 (±0.432) (n=20) | 13.1 (±6.76) (n=20) | 29.2 (±11.9) (n=20)
Late (Greater than 6 months) | 1.5 g/oral | 1.54 (±0.51) (n=6) | 19.3 (±11.7) (n=6) | 49.3 (±14.8) (n=6)

aAUC(0-12h) values quoted are extrapolated from data from samples collected over 4 hours.

In the early post-transplant period (less than 40 days post-transplant), kidney, heart, and liver transplant patients had mean MPA AUCs approximately 20% to 41% lower and mean C maxapproximately 32% to 44% lower compared to the late transplant period (i.e., 3 to 6 months post-transplant) (non-stationarity in MPA pharmacokinetics).

In liver transplant patients, administration of 1.5 g twice daily oral MMF resulted in mean MPA AUC estimates similar to those found in kidney transplant patients administered 1 g MMF twice daily.

Effect of Food

Food (27 g fat, 650 calories) had no effect on the extent of absorption (MPA AUC) of MMF when administered at doses of 1.5 g twice daily to kidney transplant patients. However, MPA C maxwas decreased by 40% in the presence of food [see Dosage and Administration (2.1)].

Distribution

The mean (±SD) apparent volume of distribution of MPA in 12 healthy volunteers was approximately 3.6 (±1.5) L/kg. At clinically relevant concentrations, MPA is 97% bound to plasma albumin. The phenolic glucuronide metabolite of MPA (MPAG) is 82% bound to plasma albumin at MPAG concentration ranges that are normally seen in stable kidney transplant patients; however, at higher MPAG concentrations (observed in patients with kidney impairment or delayed kidney graft function), the binding of MPA may be reduced as a result of competition between MPAG and MPA for protein binding. Mean blood to plasma ratio of radioactivity concentrations was approximately 0.6 indicating that MPA and MPAG do not extensively distribute into the cellular fractions of blood.

In vitro studies to evaluate the effect of other agents on the binding of MPA to human serum albumin (HSA) or plasma proteins showed that salicylate (at 25 mg/dL with human serum albumin) and MPAG (at ≥ 460 mcg/mL with plasma proteins) increased the free fraction of MPA. MPA at concentrations as high as 100 mcg/mL had little effect on the binding of warfarin, digoxin or propranolol, but decreased the binding of theophylline from 53% to 45% and phenytoin from 90% to 87%.

Elimination

Mean (±SD) apparent half-life and plasma clearance of MPA are 17.9 (±6.5) hours and 193 (±48) mL/min following oral administration.

Metabolism

MPA is metabolized principally by glucuronyl transferase to form MPAG, which is not pharmacologically active. In vivo, MPAG is converted to MPA during enterohepatic recirculation. The following metabolites of the 2-hydroxyethyl-morpholino moiety are also recovered in the urine following oral administration of MMF to healthy subjects: N-(2-carboxymethyl)-morpholine, N-(2-hydroxyethyl)- morpholine, and the N-oxide of N-(2-hydroxyethyl)-morpholine.

Due to the enterohepatic recirculation of MPAG/MPA, secondary peaks in the plasma MPA concentration-time profile are usually observed 6 to 12 hours post-dose. Bile sequestrants, such as cholestyramine, reduce MPA AUC by interfering with this enterohepatic recirculation of the drug [see Overdosage (10)and Drug Interaction Studiesbelow ].

Excretion

Negligible amount of drug is excreted as MPA (less than 1% of dose) in the urine. Orally administered radiolabeled MMF resulted in complete recovery of the administered dose, with 93% of the administered dose recovered in the urine and 6% recovered in feces. Most (about 87%) of the administered dose is excreted in the urine as MPAG. At clinically encountered concentrations, MPA and MPAG are usually not removed by hemodialysis. However, at high MPAG plasma concentrations (> 100 mcg/mL), small amounts of MPAG are removed.

Increased plasma concentrations of MMF metabolites (MPA 50% increase and MPAG about a 3-fold to 6-fold increase) are observed in patients with renal insufficiency [see Specific Populations].

Specific Populations

Patients with Renal Impairment

The mean (±SD) pharmacokinetic parameters for MPA following the administration of oral MMF given as single doses to non-transplant subjects with renal impairment are presented in Table 7.

Plasma MPA AUC observed after oral dosing to volunteers with severe chronic renal impairment (GFR < 25 mL/min/1.73 m ^2) was about 75% higher relative to that observed in healthy volunteers (GFR > 80 mL/min/1.73 m ^2). In addition, the single-dose plasma MPAG AUC was 3-fold to 6-fold higher in volunteers with severe renal impairment than in volunteers with mild renal impairment or healthy volunteers, consistent with the known renal elimination of MPAG. No data are available on the safety of long-term exposure to this level of MPAG. Multiple dosing of MMF in patients with severe chronic renal impairment has not been studied.

Patients with Delayed Graft Function or Nonfunction

In patients with delayed renal graft function post-transplant, mean MPA AUC(0-12h) was comparable to that seen in post-transplant patients without delayed renal graft function. There is a potential for a transient increase in the free fraction and concentration of plasma MPA in patients with delayed renal graft function. However, dose adjustment does not appear to be necessary in patients with delayed renal graft function. Mean plasma MPAG AUC(0-12h) was 2-fold to 3-fold higher than in post-transplant patients without delayed renal graft function [see Dosage and Administration (2.5)].

In eight patients with primary graft non-function following kidney transplantation, plasma concentrations of MPAG accumulated about 6-fold to 8-fold after multiple dosing for 28 days. Accumulation of MPA was about 1-fold to 2-fold.

The pharmacokinetics of MMF are not altered by hemodialysis. Hemodialysis usually does not remove MPA or MPAG. At high concentrations of MPAG (> 100 mcg/mL), hemodialysis removes only small amounts of MPAG.

Patients with Hepatic Impairment

The mean (± SD) pharmacokinetic parameters for MPA following the administration of oral MMF given as single doses to non-transplant subjects with hepatic impairment is presented in Table 7.

In a single-dose (1 g oral) study of 18 volunteers with alcoholic cirrhosis and 6 healthy volunteers, hepatic MPA glucuronidation processes appeared to be relatively unaffected by hepatic parenchymal disease when pharmacokinetic parameters of healthy volunteers and alcoholic cirrhosis patients within this study were compared. However, it should be noted that for unexplained reasons, the healthy volunteers in this study had about a 50% lower AUC as compared to healthy volunteers in other studies, thus making comparisons between volunteers with alcoholic cirrhosis and healthy volunteers difficult.

Table 7 Pharmacokinetic Parameters for MPA [mean (±SD)] Following Single Doses of MMF Capsules in Chronic Renal and Hepatic Impairment
Pharmacokinetic Parameters for Renal Impairment
 | Dose | T max (h) | C max (mcg/mL) | AUC(0-96h) (mcg∙h/mL)
Healthy Volunteers GFR greater than 80 mL/min/1.73 m ^2 (n=6) | 1 g | 0.75 (±0.27) | 25.3 (±7.99) | 45.0 (±22.6)
Mild Renal Impairment GFR 50 to 80 mL/min/1.73 m ^2 (n=6) | 1 g | 0.75 (±0.27) | 26.0 (±3.82) | 59.9 (±12.9)
Moderate Renal Impairment GFR 25 to 49 mL/min/1.73 m ^2 (n=6) | 1 g | 0.75 (±0.27) | 19.0 (±13.2) | 52.9 (±25.5)
Severe Renal Impairment GFR less than 25 mL/min/1.73 m ^2 (n=7) | 1 g | 1.00 (±0.41) | 16.3 (±10.8) | 78.6 (±46.4)
Pharmacokinetic Parameters for Hepatic Impairment
 | Dose | T max (h) | C max (mcg/mL) | AUC(0-48h) (mcg∙h/mL)
Healthy Volunteers (n=6) | 1 g | 0.63 (±0.14) | 24.3 (±5.73) | 29.0 (±5.78)
Alcoholic Cirrhosis (n=18) | 1 g | 0.85 (±0.58) | 22.4 (±10.1) | 29.8 (±10.7)

Pediatric Patients

The pharmacokinetic parameters of MPA and MPAG have been evaluated in 55 pediatric patients (ranging from 1 year to 18 years of age) receiving MMF oral suspension at a dose of 600 mg/m ^2twice daily (up to a maximum of 1 g twice daily) after allogeneic kidney transplantation. The pharmacokinetic data for MPA is provided in Table 8.

Table 8 Mean (±SD) Computed Pharmacokinetic Parameters for MPA by Age and Time After Allogeneic Kidney Transplantation
Age Group | (n) | Time | T max (h) |  | Dose Adjusted aC max (mcg/mL) |  | Dose Adjusted aAUC 0-12 (mcg∙h/mL)
 |  | Early (Day 7)
1 to less than 2 yr | (6) d |  | 3.03 | (4.70) | 10.3 | (5.80) | 22.5 | (6.66)
1 to less than 6 yr | (17) |  | 1.63 | (2.85) | 13.2 | (7.16) | 27.4 | (9.54)
6 to less than 12 yr | (16) |  | 0.940 | (0.546) | 13.1 | (6.30) | 33.2 | (12.1)
12 to 18 yr | (21) |  | 1.16 | (0.830) | 11.7 | (10.7) | 26.3 | (9.14) b
 |  | Late (Month 3)
1 to less than 2 yr | (4) d |  | 0.725 | (0.276) | 23.8 | (13.4) | 47.4 | (14.7)
1 to less than 6 yr | (15) |  | 0.989 | (0.511) | 22.7 | (10.1) | 49.7 | (18.2)
6 to less than 12 yr | (14) |  | 1.21 | (0.532) | 27.8 | (14.3) | 61.9 | (19.6)
12 to 18 yr | (17) |  | 0.978 | (0.484) | 17.9 | (9.57) | 53.6 | (20.3) c
 |  | Late (Month 9)
1 to less than 2 yr | (4) d |  | 0.604 | (0.208) | 25.6 | (4.25) | 55.8 | (11.6)
1 to less than 6 yr | (12) |  | 0.869 | (0.479) | 30.4 | (9.16) | 61.0 | (10.7)
6 to less than 12 yr | (11) |  | 1.12 | (0.462) | 29.2 | (12.6) | 66.8 | (21.2)
12 to 18 yr | (14) |  | 1.09 | (0.518) | 18.1 | (7.29) | 56.7 | (14.0)

aadjusted to a dose of 600 mg/m ^2
bn=20
cn=16
da subset of 1 to < 6 yr

The MMF oral suspension dose of 600 mg/m ^2twice daily (up to a maximum of 1 g twice daily) achieved mean MPA AUC values in pediatric patients similar to those seen in adult kidney transplant patients receiving oral doses of 1 g twice daily in the early post-transplant period. There was wide variability in the data. As observed in adults, early post-transplant MPA AUC values were approximately 45% to 53% lower than those observed in the later post-transplant period (>3 months). MPA AUC values were similar in the early and late post-transplant period across the 1 to 18-year age range.

A comparison of dose-normalized (to 600 mg/m ^2) MPA AUC values in 12 pediatric kidney transplant patients less than 6 years of age at 9 months post-transplant with those values in 7 pediatric liver transplant patients [median age 17 months (range: 10 – 60 months)] and at 6 months and beyond post-transplant revealed that, at the same dose, there were on average 23% lower AUC values in the pediatric liver compared to pediatric kidney patients. This is consistent with the need for higher dosing in adult liver transplant patients compared to kidney transplant patients to achieve the same exposure.

In adult transplant patients administered the same dosage of MMF, there is similar MPA exposure among kidney transplant and heart transplant patients. Based on the established similarity in MPA exposure between pediatric kidney transplant and adult kidney transplant patients at their respective approved doses, it is expected that MPA exposure at the recommended dosage will be similar in pediatric heart transplant and adult heart transplant patients.

Male and Female Patients

Data obtained from several studies were pooled to look at any gender-related differences in the pharmacokinetics of MPA (data were adjusted to 1 g oral dose). Mean (±SD) MPA AUC (0-12h) for males (n=79) was 32.0 (±14.5) and for females (n=41) was 36.5 (±18.8) mcg∙h/mL while mean (±SD) MPA C maxwas 9.96 (±6.19) in the males and 10.6 (±5.64) mcg/mL in the females. These differences are not of clinical significance.

Geriatric Patients

The pharmacokinetics of MMF and its metabolites have not been found to be altered in geriatric transplant patients when compared to younger transplant patients.

Drug Interaction Studies

Acyclovir

Coadministration of MMF (1 g) and acyclovir (800 mg) to 12 healthy volunteers resulted in no significant change in MPA AUC and C max. However, MPAG and acyclovir plasma AUCs were increased 10.6% and 21.9%, respectively.

Antacids with Magnesium and Aluminum Hydroxides

Absorption of a single dose of MMF (2 g) was decreased when administered to 10 rheumatoid arthritis patients also taking Maalox ®TC (10 mL qid). The C maxand AUC(0-24h) for MPA were 33% and 17% lower, respectively, than when MMF was administered alone under fasting conditions.

Proton Pump Inhibitors (PPIs)

Coadministration of PPIs (e.g., lansoprazole, pantoprazole) in single doses to healthy volunteers and multiple doses to transplant patients receiving MMF has been reported to reduce the exposure to MPA. An approximate reduction of 30 to 70% in the C maxand 25% to 35% in the AUC of MPA has been observed, possibly due to a decrease in MPA solubility at an increased gastric pH.

Cholestyramine

Following single-dose administration of 1.5 g MMF to 12 healthy volunteers pretreated with 4 g three times a day of cholestyramine for 4 days, MPA AUC decreased approximately 40%. This decrease is consistent with interruption of enterohepatic recirculation which may be due to binding of recirculating MPAG with cholestyramine in the intestine.

Cyclosporine

Cyclosporine (Sandimmune ®) pharmacokinetics (at doses of 275 to 415 mg/day) were unaffected by single and multiple doses of 1.5 g twice daily of MMF in 10 stable kidney transplant patients. The mean (±SD) AUC(0-12h) and C maxof cyclosporine after 14 days of multiple doses of MMF were 3290 (±822) ng∙h/mL and 753 (±161) ng/mL, respectively, compared to 3245 (±1088) ng∙h/mL and 700 (±246) ng/mL, respectively, 1 week before administration of MMF.

Cyclosporine A interferes with MPA enterohepatic recirculation. In kidney transplant patients, mean MPA exposure (AUC(0-12h)) was approximately 30-50% greater when MMF was administered without cyclosporine compared with when MMF was coadministered with cyclosporine. This interaction is due to cyclosporine inhibition of multidrug-resistance-associated protein 2 (MRP-2) transporter in the biliary tract, thereby preventing the excretion of MPAG into the bile that would lead to enterohepatic recirculation of MPA. This information should be taken into consideration when MMF is used without cyclosporine.

Drugs Affecting Glucuronidation

Concomitant administration of drugs inhibiting glucuronidation of MPA may increase MPA exposure (e.g., increase of MPA AUC (0-∞) by 35% was observed with concomitant administration of isavuconazole).

Concomitant administration of telmisartan and MMF resulted in an approximately 30% decrease in MPA concentrations. Telmisartan changes MPA's elimination by enhancing PPAR gamma (peroxisome proliferator- activated receptor gamma) expression, which in turn results in an enhanced UGT1A9 expression and glucuronidation activity.

Ganciclovir

Following single-dose administration to 12 stable kidney transplant patients, no pharmacokinetic interaction was observed between MMF (1.5 g) and intravenous ganciclovir (5 mg/kg). Mean (±SD) ganciclovir AUC and C max(n=10) were 54.3 (±19.0) mcg∙h/mL and 11.5 (±1.8) mcg/mL, respectively, after coadministration of the two drugs, compared to 51.0 (±17.0) mcg∙h/mL and 10.6 (±2.0) mcg/mL, respectively, after administration of intravenous ganciclovir alone. The mean (±SD) AUC and C maxof MPA (n=12) after coadministration were 80.9 (±21.6) mcg∙h/mL and 27.8 (±13.9) mcg/mL, respectively, compared to values of 80.3 (±16.4) µg∙h/mL and 30.9 (±11.2) mcg/mL, respectively, after administration of MMF alone.

Oral Contraceptives

A study of coadministration of MMF (1 g twice daily) and combined oral contraceptives containing ethinylestradiol (0.02 mg to 0.04 mg) and levonorgestrel (0.05 mg to 0.20 mg), desogestrel (0.15 mg) or gestodene (0.05 mg to 0.10 mg) was conducted in 18 women with psoriasis over 3 consecutive menstrual cycles. Mean serum levels of LH, FSH and progesterone were not significantly affected. Mean AUC(0-24h) was similar for ethinylestradiol and 3-keto desogestrel; however, mean levonorgestrel AUC(0-24h) significantly decreased by about 15%. There was large inter-patient variability (%CV in the range of 60% to 70%) in the data, especially for ethinylestradiol.

Sevelamer

Concomitant administration of sevelamer and MMF in adult and pediatric patients decreased the mean MPA C maxand AUC (0-12h) by 36% and 26% respectively.

Antimicrobials

Antimicrobials eliminating beta-glucuronidase-producing bacteria in the intestine (e.g. aminoglycoside, cephalosporin, fluoroquinolone, and penicillin classes of antimicrobials) may interfere with the MPAG/MPA enterohepatic recirculation thus leading to reduced systemic MPA exposure. Information concerning antibiotics is as follows:

- Trimethoprim/Sulfamethoxazole: Following single-dose administration of MMF (1.5 g) to 12 healthy male volunteers on day 8 of a 10-day course of trimethoprim 160 mg/sulfamethoxazole 800 mg administered twice daily, no effect on the bioavailability of MPA was observed. The mean (±SD) AUC and C maxof MPA after concomitant administration were 75.2 (±19.8) mcg∙h/mL and 34.0 (±6.6) µg/mL, respectively, compared to 79.2 (±27.9) mcg∙h/mL and 34.2 (±10.7) mcg/mL, respectively, after administration of MMF alone.
- Norfloxacin and Metronidazole: Following single-dose administration of MMF (1 g) to 11 healthy volunteers on day 4 of a 5-day course of a combination of norfloxacin and metronidazole, the mean MPA AUC(0-48h) was significantly reduced by 33% compared to the administration of MMF alone (p<0.05). The mean (±SD) MPA AUC(0-48h) after coadministration of MMF with norfloxacin or metronidazole separately was 48.3 (±24) mcg∙h/mL and 42.7 (±23) mcg∙h/mL, respectively, compared with 56.2 (±24) mcg∙h/mL after administration of MMF alone.
- Ciprofloxacin and Amoxicillin Plus Clavulanic Acid :A total of 64 MMF -treated kidney transplant recipients received either oral ciprofloxacin 500 mg twice daily or amoxicillin plus clavulanic acid 375 mg three times daily for 7 or at least 14 days, respectively. Approximately 50% reductions in median trough MPA concentrations (pre-dose) from baseline (MMF alone) were observed in 3 days following commencement of oral ciprofloxacin or amoxicillin plus clavulanic acid. These reductions in trough MPA concentrations tended to diminish within 14 days of antimicrobial therapy and ceased within 3 days of discontinuation of antibiotics.
- Rifampin: In a single heart-lung transplant patient, after correction for dose, a 67% decrease in MPA exposure (AUC(0-12h)) has been observed with concomitant administration of MMF and rifampin.

13 NONCLINICAL TOXICOLOGY

13.1 Carcinogenesis, Mutagenesis, Impairment of Fertility

In a 104-week oral carcinogenicity study in mice, MMF in daily doses up to 180 mg/kg was not tumorigenic. The highest dose tested was 0.2 times the recommended clinical dose (2 g/day) in renal transplant patients and 0.15 times the recommended clinical dose (3 g/day) in cardiac transplant patients when corrected for differences in body surface area (BSA). In a 104-week oral carcinogenicity study in rats, MMF in daily doses up to 15 mg/kg was not tumorigenic. The highest dose was 0.035 times the recommended clinical dose in kidney transplant patients and 0.025 times the recommended clinical dose in heart transplant patients when corrected for BSA. While these animal doses were lower than those given to patients, they were maximal in those species and were considered adequate to evaluate the potential for human risk [see Warnings and Precautions (5.2)].

The genotoxic potential of MMF was determined in five assays. MMF was genotoxic in the mouse lymphoma/thymidine kinase assay and the in vivo mouse micronucleus assay. MMF was not genotoxic in the bacterial mutation assay, the yeast mitotic gene conversion assay or the Chinese hamster ovary cell chromosomal aberration assay.

MMF had no effect on fertility of male rats at oral doses up to 20 mg/kg/day. This dose represents 0.05 times the recommended clinical dose in renal transplant patients and 0.03 times the recommended clinical dose in cardiac transplant patients when corrected for BSA. In a female fertility and reproduction study conducted in rats, oral doses of 4.5 mg/kg/day caused malformations (principally of the head and eyes) in the first generation offspring in the absence of maternal toxicity. This dose was 0.01 times the recommended clinical dose in renal transplant patients and 0.005 times the recommended clinical dose in cardiac transplant patients when corrected for BSA. No effects on fertility or reproductive parameters were evident in the dams or in the subsequent generation.

14 CLINICAL STUDIES

14.1 Kidney Transplantation

Adults

The three de novo kidney transplantation studies compared two dose levels of oral mycophenolate mofetil (1 g twice daily and 1.5 g twice daily) with azathioprine (2 studies) or placebo (1 study) to prevent acute rejection episodes. One of the two studies with azathioprine (AZA) control arm also included anti-thymocyte globulin (ATGAM ®) induction therapy. The geographic location of the investigational sites of these studies are included in Table 9.

In all three de novo kidney transplantation studies, the primary efficacy endpoint was the proportion of patients in each treatment group who experienced treatment failure within the first 6 months after transplantation. Treatment failure was defined as biopsy-proven acute rejection on treatment or the occurrence of death, graft loss or early termination from the study for any reason without prior biopsy-proven rejection.

Mycophenolate mofetil, in combination with corticosteroids and cyclosporine, reduced (statistically significant at 0.05 level) the incidence of treatment failure within the first 6 months following transplantation (Table 9). Patients who prematurely discontinued treatment were followed for the occurrence of death or graft loss, and the cumulative incidence of graft loss and patient death combined are summarized in Table 10. Patients who prematurely discontinued treatment were not followed for the occurrence of acute rejection after termination.

Table 9 Treatment Failure in De Novo Kidney Transplantation Studies
USA Study | MYCOPHENOLATE MOFETIL 2 g/day | MYCOPHENOLATE MOFETIL 3 g/day | AZA 1 to 2 mg/kg/day
(N=499 patients) | (n=167 patients) | (n=166 patients) | (n=166 patients)
 | All 3 groups received anti-thymocyte globulin induction, cyclosporine and corticosteroids
All treatment failures | 31.1% | 31.3% | 47.6%
Early termination without prior acute rejection | 9.6% | 12.7% | 6.0%
Biopsy-proven rejection episode on treatment | 19.8% | 17.5% | 38.0%
Europe/Canada/Australia Study (N=503 patients) | MYCOPHENOLATE MOFETIL 2 g/day (n=173 patients) | MYCOPHENOLATE MOFETIL 3 g/day (n=164 patients) | AZA 100 to 150 mg/day (n=166 patients)
Europe/Canada/Australia Study (N=503 patients) | No induction treatment administered; all 3 groups received cyclosporine and corticosteroids.
All treatment failures | 38.2% | 34.8% | 50.0%
Early termination without prior acute rejection | 13.9% | 15.2% | 10.2%
Biopsy-proven rejection episode on treatment | 19.7% | 15.9% | 35.5%
Europe Study | MYCOPHENOLATE MOFETIL 2 g/day | MYCOPHENOLATE MOFETIL 3 g/day | Placebo
(N=491 patients) | (n=165 patients) | (n=160 patients) | (n=166 patients)
 | No induction treatment administered; all 3 groups received cyclosporine and corticosteroids.
All treatment failures | 30.3% | 38.8% | 56.0%
Early termination without prior acute rejection | 11.5% | 22.5% | 7.2%
Biopsy-proven rejection episode on treatment | 17.0% | 13.8% | 46.4%

*Does not include death and graft loss as reason for early termination.

No advantage of mycophenolate mofetil at 12 months with respect to graft loss or patient death (combined) was established (Table 10). Numerically, patients receiving mycophenolate mofetil 2 g/day and 3 g/day experienced a better outcome than controls in all three studies; patients receiving mycophenolate mofetil 2 g/day experienced a better outcome than mycophenolate mofetil 3 g/day in two of the three studies. Patients in all treatment groups who terminated treatment early were found to have a poor outcome with respect to graft loss or patient death at 1 year.

Table 10 De Novo Kidney Transplantation Studies Cumulative Incidence of Combined Graft Loss or Patient Death at 12 Months
Study | MYCOPHENOLATE MOFETIL 2 g/day | MYCOPHENOLATE MOFETIL 3 g/day | Control (AZA or Placebo)
USA | 8.5% | 11.5% | 12.2%
Europe/Canada/Australia | 11.7% | 11.0% | 13.6%
Europe | 8.5% | 10.0% | 11.5%

Pediatrics- De Novo Kidney transplantation PK Study with Long Term Follow-Up One open-label, safety and pharmacokinetic study of mycophenolate mofetil oral suspension 600 mg/m ^2twice daily (up to 1 g twice daily) in combination with cyclosporine and corticosteroids was performed at centers in the United States (9), Europe (5) and Australia (1) in 100 pediatric patients (3 months to 18 years of age) for the prevention of renal allograft rejection. Mycophenolate mofetil was well tolerated in pediatric patients [see Adverse Reactions (6.1)]. The rate of biopsy-proven rejection was similar across the age groups (3 months to <6 years, 6 years to <12 years, 12 years to 18 years). The overall biopsy-proven rejection rate at 6 months was comparable to adults. The combined incidence of graft loss (5%) and patient death (2%) at 12 months post-transplant was similar to that observed in adult kidney transplant patients.

14.2 Heart Transplantation

A double-blind, randomized, comparative, parallel-group, multicenter study in primary de novo heart transplant recipients was performed at centers in the United States (20), in Canada (1), in Europe (5) and in Australia (2). The total number of patients enrolled (ITT population) was 650; 72 never received study drug and 578 received study drug (Safety Population). Patients received mycophenolate mofetil 1.5 g twice daily (n=289) or AZA 1.5 to 3 mg/kg/day (n=289), in combination with cyclosporine (Sandimmune ®or Neoral ®) and corticosteroids as maintenance immunosuppressive therapy. The two primary efficacy endpoints were: (1) the proportion of patients who, after transplantation, had at least one endomyocardial biopsy-proven rejection with hemodynamic compromise, or were re-transplanted or died, within the first 6 months, and (2) the proportion of patients who died or were re-transplanted during the first 12 months following transplantation. Patients who prematurely discontinued treatment were followed for the occurrence of allograft rejection for up to 6 months and for the occurrence of death for 1 year.

The analyses of the endpoints showed:

- Rejection: No difference was established between mycophenolate mofetil and AZA with respect to biopsy-proven rejection with hemodynamic compromise.
- Survival: Mycophenolate mofetil was shown to be at least as effective as AZA in preventing death or re-transplantation at 1 year (see Table 11).

Table 11 De Novo Heart Transplantation Study Rejection at 6 Months/Death or Re-transplantation at 1 Year
 | All Patients (ITT) |  | Treated Patients
 | AZA N = 323 | MYCOPHENOLATE MOFETIL N = 327 | AZA N = 289 | MYCOPHENOLATE MOFETIL N = 289
Biopsy-proven rejection with hemodynamic compromise at 6 months a | 121 (38%) | 120 (37%) | 100 (35%) | 92 (32%)
Death or re-transplantation at 1 year | 49 (15.2%) | 42 (12.8%) | 33 (11.4%) | 18 (6.2%)

aHemodynamic compromise occurred if any of the following criteria were met: pulmonary capillary wedge pressure ≥20 mm or a 25% increase; cardiac index <2.0 L/min/m ^2or a 25% decrease; ejection fraction ≤30%; pulmonary artery oxygen saturation ≤60% or a 25% decrease; presence of new S 3gallop; fractional shortening was ≤20% or a 25% decrease; inotropic support required to manage the clinical condition.

14.3 Liver Transplantation

A double-blind, randomized, comparative, parallel-group, multicenter study in primary hepatic transplant recipients was performed at centers in the United States (16), in Canada (2), in Europe (4) and in Australia (1). The total number of patients enrolled was 565. Per protocol, patients received mycophenolate mofetil 1.5 g twice daily orally or AZA 1 to 2 mg/kg/day orally, in combination with cyclosporine (Neoral ®) and corticosteroids as maintenance immunosuppressive therapy. The actual median oral dose of AZA on study was 1.5 mg/kg/day (range of 0.3 to 3.8 mg/kg/day) initially and 1.26 mg/kg/day (range of 0.3 to 3.8 mg/kg/day) at 12 months. The two primary endpoints were: (1) the proportion of patients who experienced, in the first 6 months post-transplantation, one or more episodes of biopsy-proven and treated rejection or death or re-transplantation, and (2) the proportion of patients who experienced graft loss (death or re-transplantation) during the first 12 months post-transplantation. Patients who prematurely discontinued treatment were followed for the occurrence of allograft rejection and for the occurrence of graft loss (death or re-transplantation) for 1 year.

In combination with corticosteroids and cyclosporine, mycophenolate mofetil demonstrated a lower rate of acute rejection at 6 months and a similar rate of death or re-transplantation at 1 year compared to AZA (Table 12).

Table 12 De Novo Liver Transplantation Study Rejection at 6 Months/Death or Retransplantation at 1 Year
 | AZA N = 287 | MYCOPHENOLATE MOFETIL N = 278
Biopsy-proven, treated rejection at 6 months (includes death or re-transplantation) | 137 (47.7%) | 107 (38.5%)
Death or re-transplantation at 1 year | 42 (14.6%) | 41 (14.7%)

15 REFERENCES

1. “OSHA Hazardous Drugs.” OSHA. http://www.osha.gov/SLTC/hazardousdrugs/index.html

16 HOW SUPPLIED/STORAGE AND HANDLING

Handling and Disposal

Mycophenolate mofetil has demonstrated teratogenic effects in humans [see Warnings and Precautions (5.1) and Use in Specific Populations (8.1)] . Wearing disposable gloves is recommended when wiping the outer surface of the bottle and or bottle cap. Avoid direct contact of MYHIBBIN with skin or mucous membranes [see Dosage and Administration(2.1)]. Follow applicable special handling and disposal procedures ^1. Do not use after 60 days of first opening the bottle.

STORAGE AND HANDLING

MYHIBBIN is supplied as a white to off-white oral suspension of mycophenolate mofetil 200 mg/mL and it is supplied with a child resistant cap:

- 175 mL of suspension in 225 mL bottle.............................................. NDC 24338-018-01

Storage and Stability

- Store at 20°C to 25°C (68°F to 77°F); excursions permitted to 15°C to 30°C (59°F to 86°F) [See USP Controlled Room Temperature].
- Do not freeze.

17 PATIENT COUNSELING INFORMATION

Advise the patient to read the FDA-approved patient labeling (Medication Guide).

17.1 Embryofetal Toxicity

Pregnancy loss and malformation

- Inform females of reproductive potential and pregnant women that use of MYHIBBIN during pregnancy is associated with an increased risk of first trimester pregnancy loss and an increased risk of congenital malformations. Advise that they must use an acceptable form of contraception [see Warnings and Precautions (5.1), Use in Specific Populations (8.1, 8.3)].
- Encourage pregnant women to enroll in the Pregnancy Exposure Registry. This registry monitors pregnancy outcomes in women exposed to mycophenolate [see Use in Specific Populations (8.1)].

Contraception

- Discuss pregnancy testing, pregnancy prevention and planning with females of reproductive potential [see Use in Specific Populations (8.3)].
- Females of reproductive potential must use an acceptable form of birth control during the entire MYHIBBIN therapy and for 6 weeks after stopping MYHIBBIN, unless the patient chooses abstinence. MYHIBBIN may reduce effectiveness of oral contraceptives. Use of additional barrier contraceptive methods is recommended [see Use in Specific Populations (8.3)].
- For patients who are considering pregnancy, discuss appropriate alternative immunosuppressants with less potential for embryofetal toxicity. Risks and benefits of MYHIBBIN should be discussed with the patient.
- Advise sexually active male patients and/or their partners to use effective contraception during the treatment of the male patient and for at least 90 days after cessation of treatment. This recommendation is based on findings of animal studies [see Use in Specific Populations (8.3), Nonclinical Toxicology (13.1)].

17.2 Development of Lymphoma and Other Malignancies

- Inform patients that they are at increased risk of developing lymphomas and other malignancies, particularly of the skin, due to immunosuppression [see Warnings and Precautions (5.2)].
- Advise patients to limit exposure to sunlight and ultraviolet (UV) light by wearing protective clothing and use of broad-spectrum sunscreen with high protection factor.

17.3 Increased Risk of Serious Infections

Inform patients that they are at increased risk of developing a variety of infections due to immunosuppression. Instruct them to contact their physician if they develop any of the signs and symptoms of infection explained in the Medication Guide [see Warnings and Precautions (5.3)].

17.4 Blood Dyscrasias

Inform patients that they are at increased risk for developing blood adverse effects such as anemia or low white blood cells. Advise patients to immediately contact their healthcare provider if they experience any evidence of infection, unexpected bruising, or bleeding, or any other manifestation of bone marrow suppression [see Warnings and Precautions (5.4)].

17.5 Gastrointestinal Tract Complications

Inform patients that MYHIBBIN can cause gastrointestinal tract complications including bleeding, intestinal perforations, and gastric or duodenal ulcers. Advise the patient to contact their healthcare provider if they have symptoms of gastrointestinal bleeding, or sudden onset or persistent abdominal pain [see Warnings and Precautions (5.5)].

17.6 Acute Inflammatory Syndrome

Inform patients that acute inflammatory reactions have been reported in some patients who received mycophenolate mofetil. Some reactions were severe, requiring hospitalization. Advise patients to contact their physician if they develop fever, joint stiffness, joint pain or muscle pains [see Warnings and Precautions (5.7)].

17.7 Hypersensitivity Reactions

Inform patients of the potential risk of hypersensitivity reactions. Advise patients to stop taking MYHIBBIN and seek immediate medical attention if signs or symptoms of a hypersensitivity reaction occur (such as swelling of face, lips, tongue, or throat; difficulty breathing or swallowing) [see Warning and Precautions (5.8)].

17.8 Immunizations

Inform patients that MYHIBBIN can interfere with the usual response to immunizations. Before seeking vaccines on their own, advise patients to discuss first with their physician [see Warnings and Precautions (5.9)].

17.9 Administration Instructions

- Advise patients to avoid contact of the skin or mucous membranes with MYHIBBIN. If such contact occurs, they must wash the area of contact thoroughly with soap and water. In case of ocular contact, rinse eyes with plain water.
- Advise patients to take a missed dose as soon as they remember, except if it is closer than 2 hours to the next scheduled dose; in this case they should continue to take MYHIBBIN at the usual times.

17.10 Blood Donation

Advise patients not to donate blood during therapy and for at least 6 weeks following discontinuation of MYHIBBIN [see Warnings and Precautions (5.10)].

17.11 Semen Donation

Advise males of childbearing potential not to donate semen during therapy and for 90 days following discontinuation of MYHIBBIN [see Warnings and Precautions (5.11)].

17.12 Potential to Impair Driving and Use of Machinery

Advise patients that MYHIBBIN can affect the ability to drive or operate machines. Patients should avoid driving or operating machines if they experience somnolence, confusion, dizziness, tremor or hypotension during treatment with MYHIBBIN [see Warnings and Precautions (5.13)].
Distributed by:
Azurity Pharmaceuticals, Inc.
Woburn, MA 01801 USA
MYH-PI-02 Rev. 04/2025

SPL MEDGUIDE SECTION

MEDICATION GUIDE
MYHIBBIN™ (my hib in)
(mycophenolate mofetil oral suspension)

Read the Medication Guide that comes with MYHIBBIN before you start taking it and each time you refill your prescription. There may be new information. This Medication Guide does not take the place of talking with your doctor about your medical condition or treatment.

What is the most important information I should know about MYHIBBIN?
MYHIBBIN can cause serious side effects, including:
Increased risk of loss of a pregnancy (miscarriage) and higher risk of birth defects. Females who take MYHIBBIN during pregnancy have a higher risk of miscarriage during the first 3 months (first trimester), and a higher risk that their baby will be born with birth defects.

- If you are a female who can become pregnant, your healthcare provider must talk with you about acceptable birth control methods (contraceptive counseling) to use while taking MYHIBBIN. You should have 1 pregnancy test immediately before starting MYHIBBIN and another pregnancy test 8 to 10 days later. Pregnancy tests should be repeated during routine follow-up visits with your healthcare provider. Talk to your healthcare provider about the results of all of your pregnancy tests.
  You must use acceptable birth control during your entire MYHIBBIN treatment and for 6 weeks after stopping MYHIBBIN, unless at any time you choose to avoid sexual intercourse (abstinence) with a man completely. MYHIBBIN decreases blood levels of the hormones in birth control pills that you take by mouth. Birth control pills may not work as well while you take MYHIBBIN, and you could become pregnant. If you take birth control pills while using MYHIBBIN you must also use another form of birth control. Talk to your healthcare provider about other birth control methods that you can use while taking MYHIBBIN.
- If you are a sexually active male whose female partner can become pregnant while you are taking MYHIBBIN, use effective contraception during treatment and for at least 90 days after stopping MYHIBBIN.
- If you plan to become pregnant, talk with your healthcare provider. Your healthcare provider will decide if other medicines to prevent rejection may be right for you.
- If you become pregnant while taking MYHIBBIN, do not stop taking MYHIBBIN. Call your healthcare provider right away. You and your healthcare provider may decide that other medicines to prevent rejection may be right for you. You and your healthcare provider should report your pregnancy to the Mycophenolate Pregnancy Registry either:
  o By phone at 1-800-617-8191 or
  o By visiting the REMS website at: www.mycophenolateREMS.com
  The purpose of this registry is to gather information about the health of you and your baby.

Increased risk of getting certain cancers. People who take MYHIBBIN have a higher risk of getting lymphoma, and other cancers, especially skin cancer. Tell your healthcare provider if you have:

- unexplained fever, prolonged tiredness, weight loss or lymph node swelling
- a change in the size and color of a mole
- a brown or black skin lesion with uneven borders, or one part of the lesion does not look like the other
- a new skin lesion or bump
- any other changes to your health

Increased risk of getting serious infections. MYHIBBIN weakens the body’s immune system and affects your ability to fight infections. Serious infections can happen with MYHIBBIN and can lead to hospitalizations and death. These serious infections can include:

- Viral infections. Certain viruses can live in your body and cause active infections when your immune system is weak. Viral infections that can happen with MYHIBBIN include:
  o Shingles, other herpes infections, and cytomegalovirus (CMV). CMV can cause serious tissue and blood infections.
  o BK virus. BK virus can affect how your kidney works and cause your transplanted kidney to fail.
  o Hepatitis B and C viruses. Hepatitis viruses can affect how your liver works. Talk to your healthcare provider about how hepatitis viruses may affect you.
  o COVID-19

- A brain infection called Progressive Multifocal Leukoencephalopathy (PML). In some patients, MYHIBBIN may cause an infection of the brain that may cause death. You are at risk for this brain infection because you have a weakened immune system. Call your healthcare provider right away if you have any of the following symptoms:
  o weakness on one side of the body
  o you are confused or have problems thinking
  o you do not care about things you usually care about (apathy)
  o you cannot control your muscles

- Fungal infections. Yeasts and other types of fungal infections can happen with MYHIBBIN and can cause serious tissue and blood infections (See “What are the possible side effects of MYHIBBIN?”).

Call your healthcare provider right away if you have any of the following signs and symptoms of infection:

- temperature of 100.5°F or greater
- pain during urination
- cold symptoms, such as a runny nose or sore throat
- white patches in the mouth or throat
- flu symptoms, such as an upset stomach, stomach pain, vomiting or diarrhea
- unexpected bruising or bleeding
- earache or headache
- cuts, scrapes or incisions that are red, warm and oozing pus

See “What are the possible side effects of MYHIBBIN?” for information about other serious side effects.

What is MYHIBBIN?

- MYHIBBIN is a prescription medicine to prevent rejection (antirejection medicine) in people who have received a kidney, heart or liver transplant. Rejection is when the body’s immune system perceives the new organ as a “foreign” threat and attacks it.
- MYHIBBIN is used with other medicines containing cyclosporine and corticosteroids.

Do not take MYHIBBIN if you:

- have a history of allergic reactions to mycophenolate mofetil or any of the ingredients in MYHIBBIN. See the end of this Medication Guide for a complete list of ingredients in MYHIBBIN.

Before taking MYHIBBIN tell your healthcare provider about all of your medical conditions, including if you:

- have any digestive problems, such as ulcers.
- have Lesch-Nyhan syndrome, Kelley-Seegmiller syndrome, or another rare inherited deficiency hypoxanthine guanine phosphoribosyl-transferase (HGPRT). You should not take MYHIBBIN if you have one of these disorders.
- plan to receive any vaccines. People taking MYHIBBIN should not receive live vaccines. Some vaccines may not work as well during treatment with MYHIBBIN.
- are pregnant or plan to become pregnant. See “What is the most important information I should know about MYHIBBIN?”
- are breastfeeding or plan to breastfeed. It is not known if MYHIBBIN passes into breast milk. You and your healthcare provider will decide if you will take MYHIBBIN or breastfeed.

Tell your healthcare provider about all the medicines you take, including prescription and over-the-counter medicines, vitamins and herbal supplements. Some medicines may affect the way MYHIBBIN works, and MYHIBBIN may affect how some medicines work.
Especially tell your healthcare provider if you take:

- birth control pills (oral contraceptives). See “What is the most important information I should know about MYHIBBIN?”
- sevelamer (Renagel, Renvela). These products should be taken at least 2 hours after taking MYHIBBIN.
- acyclovir (Zovirax), valacyclovir (Valtrex), ganciclovir (CYTOVENE-IV, Vitrasert), valganciclovir (VALCYTE).
- rifampin (Rifater, Rifamate, Rimactane, Rifadin).
- antacids that contain magnesium and aluminum (MYHIBBIN and the antacid should not be taken at the same time).
- proton pump inhibitors (PPIs) (Prevacid, Protonix).
- sulfamethoxazole/trimethoprim (BACTRIM, BACTRIM DS).
- norfloxacin (Noroxin®) and metronidazole (Flagyl, Flagyl ER, Flagyl IV, Metro IV, Helidac, Pylera).
- ciprofloxacin (Cipro, Cipro XR, Ciloxan, Proquin XR) and amoxicillin plus clavulanic acid (Augmentin, Augmentin XR).
- azathioprine (Azasan, Imuran).
- cholestyramine (Questran Light, Questran, Locholest Light, Locholest, Prevalite).

Know the medicines you take. Keep a list of all your medicines. Show them to your healthcare provider or pharmacist when you get a new medicine. Do not take any new medicine without talking with your doctor.

How should I take MYHIBBIN?

- Take MYHIBBIN exactly as prescribed.
- Do not stop taking MYHIBBIN or change the dose unless your healthcare provider tells you to.
- If you miss a dose of MYHIBBIN, or you are not sure when you took your last dose, take your prescribed dose of MYHIBBIN as soon as you remember. If your next dose is less than 2 hours away, skip the missed dose and take your next dose at your normal scheduled time. Do not take 2 doses at the same time. Call your healthcare provider if you are not sure what to do.
- Take MYHIBBIN on an empty stomach, unless your healthcare provider tells you otherwise.
- If you are not able to swallow mycophenolate mofetil tablets or capsules, your doctor may prescribe MYHIBBIN. This is a liquid form of mycophenolate mofetil.
- Do not mix MYHIBBIN with any other medicine. MYHIBBIN should not be mixed with any type of liquids before taking the dose.
- Do not let MYHIBBIN come in contact with your skin or mucous membranes.
  o If you accidentally get the oral suspension on the skin, wash the area well with soap and water.
  o If you accidentally get the oral suspension in your eyes or other mucous membranes, rinse with plain water.
- If you take too much MYHIBBIN, call your healthcare provider or the poison control center right away.

What should I avoid while taking MYHIBBIN?

- Avoid becoming pregnant. (See “What is the most important information I should know about MYHIBBIN?”)
- Limit the amount of time you spend in sunlight. Avoid using tanning beds or sunlamps. People who take MYHIBBIN have a higher risk of getting skin cancer (See “What is the most important information I should know about MYHIBBIN?”). Wear protective clothing when you are in the sun and use a broad-spectrum sunscreen with a high protection factor. This is especially important if your skin is very fair or if you have a family history of skin cancer.
- You should not donate blood while taking MYHIBBIN and for at least 6 weeks after stopping MYHIBBIN.
- You should not donate sperm while taking MYHIBBIN and for 90 days after stopping MYHIBBIN.
- MYHIBBIN may influence your ability to drive and use machines (See “What are the possible side effects of MYHIBBIN?”. If you experience drowsiness, confusion, dizziness, tremor, or low blood pressure during treatment with MYHIBBIN, you should be cautious about driving or using heavy machines.

What are the possible side effects of MYHIBBIN?
MYHIBBIN may cause serious side effects, including:

- See “What is the most important information I should know about MYHIBBIN?”
- Low blood cell counts. People taking high doses of MYHIBBIN each day may have a decrease in blood counts, including:
  o white blood cells, especially neutrophils. Neutrophils fight against bacterial infections. You have a higher chance of getting an infection when your white blood cell count is low. This is most common from 1 month to 6 months after your transplant.
  o red blood cells. Red blood cells carry oxygen to your body tissues. You have a higher chance of getting severe anemia when your red blood cell count is low.
  o platelets. Platelets help with blood clotting.
  Your healthcare provider will do blood tests before you start taking MYHIBBIN and during treatment with MYHIBBIN to check your blood cell counts. Tell your healthcare provider right away if you have any signs of infection (See “What is the most important information I should know about MYHIBBIN?”), including any unexpected bruising or bleeding. Also, tell your doctor if you have unusual tiredness, lack of energy, dizziness or fainting.
- Stomach problems. Stomach problems including intestinal bleeding, a tear in your intestinal wall (perforation) or stomach ulcers can happen in people who take MYHIBBIN. Bleeding can be severe and you may have to be hospitalized for treatment. Call your doctor right away if you have sudden or severe stomach-area pain or stomach- area pain that does not go away, or if you have diarrhea.
- Inflammatory reactions. Some people taking MYHIBBIN may have an inflammatory reaction with fever, joint stiffness, joint pain, and muscle pain. Some of these reactions may require hospitalization. This reaction could happen within weeks to months after your treatment with MYHIBBIN starts or if your dose is increased. Call your healthcare provider right away if you experience these symptoms.
- Allergic (hypersensitivity) reactions. Allergic reactions, including a severe allergic reaction called anaphylaxis, can happen after taking MYHIBBIN. Stop taking MYHIBBIN and get emergency medical help right away if you have any of the following symptoms of an allergic reaction:
  o swelling of the face, lips, tongue, or throat
  o trouble breathing or swallowing
  o rash, hives, or itching
  o fast heartbeat
  o fainting, dizziness, feeling lightheaded
  o chest pain

The most common side effects of MYHIBBIN include:

- diarrhea
- changes in laboratory blood levels, including high levels of blood sugar (hyperglycemia)
- blood problems including low white and red blood cell counts
- stomach problems including diarrhea, constipation, nausea and vomiting
- infections
- blood pressure problems
- rash
- fast heartbeat
- swelling of the lower legs, ankles and feet
- nervous system problems such as headache, dizziness and tremor

Side effects that can happen more often in children than in adults taking MYHIBBIN include:

- stomach area pain
- vomiting
- fever
- sore throat
- infection
- colds (respiratory tract infections)
- pain
- high blood pressure
- blood infection (sepsis)
- low white blood cell count
- diarrhea
- low red blood cell count

These are not all of the possible side effects of MYHIBBIN. Tell your doctor about any side effect that bothers you or that does not go away.
Call your doctor for medical advice about side effects. You may report side effects to FDA at 1-800-FDA-1088. You may also report side effects to Azurity Pharmaceuticals, Inc. at 1-800-461-7449.

How should I store MYHIBBIN?

- Store MYHIBBIN at 20°C to 25°C (68°F to 77°F); excursions permitted to 15°C to 30°C (59°F to 86°F) [See USP Controlled Room Temperature]. Do not freeze.
- Wear gloves when wiping the MYHIBBIN bottle and bottle cap.

Keep MYHIBBIN and all medicines out of the reach of children.

General information about the safe and effective use of MYHIBBIN.
Medicines are sometimes prescribed for purposes other than those listed in a Medication Guide. Do not use MYHIBBIN for a condition for which it was not prescribed. Do not give MYHIBBIN to other people, even if they have the same symptoms that you have. It may harm them.
This Medication Guide summarizes the most important information about MYHIBBIN. If you would like more information, talk with your doctor. You can ask your pharmacists or healthcare provider information about MYHIBBIN that is written for health professionals.

What are the ingredients in MYHIBBIN?
Active ingredient: Mycophenolate Mofetil
Inactive ingredients:
MYHIBBIN: dibasic sodium phosphate, glycerin, methylparaben, monobasic sodium phosphate, polysorbate 80, propylparaben, purified water, raspberry flavor, simethicone emulsion, sorbitol solution, and xanthan gum.
Distributed by:
Azurity Pharmaceuticals, Inc.
Woburn, MA 01801 USA

This Medication Guide has been approved by the U.S. Food and Drug Administration Approved: 04/2025
MYH-MG-02

PACKAGE LABEL.PRINCIPAL DISPLAY PANEL

MYHIBBIN Oral Suspension, 200 mg/mL - NDC 24338-018-01 - 175 mL Carton label

MYHIBBIN Oral Suspension, 200 mg/mL - NDC 24338-018-01 - 175 mL Bottle label